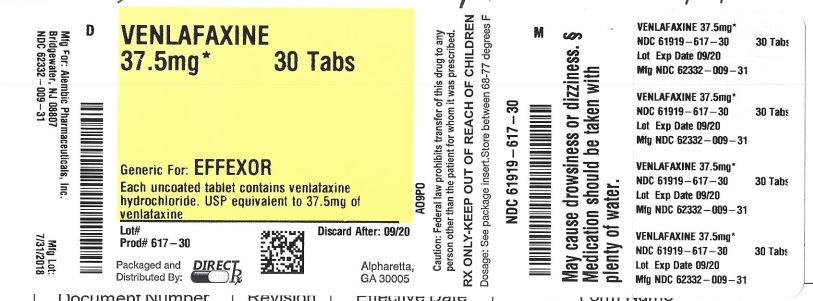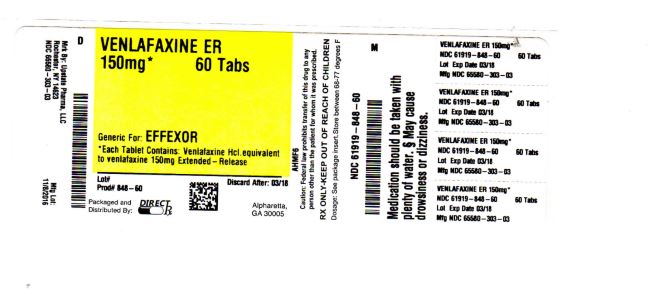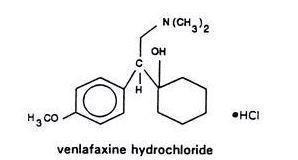 DRUG LABEL: VENLAFAXINE HYDROCHLORIDE
NDC: 61919-848 | Form: CAPSULE, EXTENDED RELEASE
Manufacturer: DIRECT RX
Category: prescription | Type: HUMAN PRESCRIPTION DRUG LABEL
Date: 20190424

ACTIVE INGREDIENTS: VENLAFAXINE HYDROCHLORIDE 150 mg/1 1
INACTIVE INGREDIENTS: POWDERED CELLULOSE; GELATIN; FERRIC OXIDE RED; TITANIUM DIOXIDE; HYPROMELLOSES; HYPROMELLOSE 2910 (6 MPA.S); ETHYLCELLULOSE (100 MPA.S)

VENLAFAXINE HYDROCHLORIDE

BOXED WARNING SECTION

Suicidality and Antidepressant Drugs

Antidepressants increased the risk compared to placebo of suicidal thinking and behavior (suicidality) in children, adolescents, and young adults in short-term studies of Major Depressive Disorder (MDD) and other psychiatric disorders. Anyone considering the use of venlafaxine hydrochloride extended-release capsules or any other antidepressant in a child, adolescent, or young adult must balance this risk with the clinical need. Short-term studies did not show an increase in the risk of suicidality with antidepressants compared to placebo in adults beyond age 24; there was a reduction in risk with antidepressants compared to placebo in adults aged 65 and older. Depression and certain other psychiatric disorders are themselves associated with increases in the risk of suicide. Patients of all ages who are started on antidepressant therapy should be monitored appropriately and observed closely for clinical worsening, suicidality, or unusual changes in behavior. Families and caregivers should be advised of the need for close observation and communication with the prescriber. Venlafaxine hydrochloride extended-release capsules are not approved for use in pediatric patients. (See WARNINGS: Clinical Worsening and Suicide Risk, PRECAUTIONS: Information for Patients, and PRECAUTIONS: Pediatric Use)

DESCRIPTION SECTION

Venlafaxine hydrochloride extended-release capsules for oral administration contain venlafaxine hydrochloride, a structurally novel antidepressant. It is designated (R/S)-1-[2-(dimethylamino)-1-(4-methoxyphenyl)ethyl] cyclohexanol hydrochloride or (±)-1-[α- [(dimethylamino)methyl]-p-methoxybenzyl] cyclohexanol hydrochloride and has the empirical formula of C17H27NO2 HCl. Its molecular weight is 313.87. The structural formula is shown below.

Venlafaxine hydrochloride is a white to off-white crystalline solid with a solubility of 572 mg/mL in water (adjusted to ionic strength of 0.2 M with sodium chloride). Its octanol:water (0.2 M sodium chloride) partition coefficient is 0.43.

Venlafaxine hydrochloride extended-release capsules are formulated as an extended-release capsule for once-a-day oral administration. Drug release is controlled by diffusion through the coating membrane on the spheroids and is not pH dependent. Capsules contain venlafaxine hydrochloride equivalent to 37.5 mg, 75 mg, or 150 mg venlafaxine. Inactive ingredients consist of cellulose, ethylcellulose, gelatin, hypromellose, iron oxide, and titanium dioxide.

CLINICAL PHARMACOLOGY SECTION

Pharmacodynamics

The mechanism of the antidepressant action of venlafaxine in humans is believed to be associated with its potentiation of neurotransmitter activity in the CNS. Preclinical studies have shown that venlafaxine and its active metabolite, O-desmethylvenlafaxine (ODV), are potent inhibitors of neuronal serotonin and norepinephrine reuptake and weak inhibitors of dopamine reuptake. Venlafaxine and ODV have no significant affinity for muscarinic cholinergic, H1-histaminergic, or α1-adrenergic receptors in vitro. Pharmacologic activity at these receptors is hypothesized to be associated with the various anticholinergic, sedative, and cardiovascular effects seen with other psychotropic drugs. Venlafaxine and ODV do not possess monoamine oxidase (MAO) inhibitory activity.

Pharmacokinetics

Steady-state concentrations of venlafaxine and ODV in plasma are attained within 3 days of oral multiple dose therapy. Venlafaxine and ODV exhibited linear kinetics over the dose range of 75 to 450 mg/day. Mean±SD steady-state plasma clearance of venlafaxine and ODV is 1.3±0.6 and 0.4±0.2 L/h/kg, respectively; apparent elimination half-life is 5±2 and 11±2 hours, respectively; and apparent (steady-state) volume of distribution is 7.5±3.7 and 5.7±1.8 L/kg, respectively. Venlafaxine and ODV are minimally bound at therapeutic concentrations to plasma proteins (27% and 30%, respectively).

Absorption

Venlafaxine is well absorbed and extensively metabolized in the liver. O-desmethylvenlafaxine (ODV) is the only major active metabolite. On the basis of mass balance studies, at least 92% of a single oral dose of venlafaxine is absorbed. The absolute bioavailability of venlafaxine is about 45%.

Administration of venlafaxine hydrochloride extended-release capsules (150 mg q24 hours) generally resulted in lower Cmax (150 ng/mL for venlafaxine and 260 ng/mL for ODV) and later Tmax (5.5 hours for venlafaxine and 9 hours for ODV) than for venlafaxine hydrochloride tablets (immediate release) [Cmax's for immediate release 75 mg q12 hours were 225 ng/mL for venlafaxine and 290 ng/mL for ODV; Tmax's were 2 hours for venlafaxine and 3 hours for ODV]. When equal daily doses of venlafaxine were administered as either an immediate release tablet or the extended-release capsule, the exposure to both venlafaxine and ODV was similar for the two treatments, and the fluctuation in plasma concentrations was slightly lower with the venlafaxine hydrochloride extended-release capsule. Venlafaxine hydrochloride extended-release capsules, therefore, provide a slower rate of absorption, but the same extent of absorption compared with the immediate release tablet.

Food did not affect the bioavailability of venlafaxine or its active metabolite, ODV. Time of administration (AM vs PM) did not affect the pharmacokinetics of venlafaxine and ODV from the 75 mg venlafaxine hydrochloride extended-release capsule.

Metabolism and Excretion

Following absorption, venlafaxine undergoes extensive presystemic metabolism in the liver, primarily to ODV, but also to N-desmethylvenlafaxine, N,O-didesmethylvenlafaxine, and other minor metabolites. In vitro studies indicate that the formation of ODV is catalyzed by CYP2D6; this has been confirmed in a clinical study showing that patients with low CYP2D6 levels (“poor metabolizers”) had increased levels of venlafaxine and reduced levels of ODV compared to people with normal CYP2D6 (“extensive metabolizers”). The differences between the CYP2D6 poor and extensive metabolizers, however, are not expected to be clinically important because the sum of venlafaxine and ODV is similar in the two groups and venlafaxine and ODV are pharmacologically approximately equiactive and equipotent.

Approximately 87% of a venlafaxine dose is recovered in the urine within 48 hours as unchanged venlafaxine (5%), unconjugated ODV (29%), conjugated ODV (26%), or other minor inactive metabolites (27%). Renal elimination of venlafaxine and its metabolites is thus the primary route of excretion.

Special Populations

Age and Gender: A population pharmacokinetic analysis of 404 venlafaxine-treated patients from two studies involving both b.i.d. and t.i.d. regimens showed that dose-normalized trough plasma levels of either venlafaxine or ODV were unaltered by age or gender differences. Dosage adjustment based on the age or gender of a patient is generally not necessary (see DOSAGE AND ADMINISTRATION).

Extensive/Poor Metabolizers: Plasma concentrations of venlafaxine were higher in CYP2D6 poor metabolizers than extensive metabolizers. Because the total exposure (AUC) of venlafaxine and ODV was similar in poor and extensive metabolizer groups, however, there is no need for different venlafaxine dosing regimens for these two groups.

Liver Disease: In 9 subjects with hepatic cirrhosis, the pharmacokinetic disposition of both venlafaxine and ODV was significantly altered after oral administration of venlafaxine. Venlafaxine elimination half-life was prolonged by about 30%, and clearance decreased by about 50% in cirrhotic subjects compared to normal subjects. ODV elimination half-life was prolonged by about 60%, and clearance decreased by about 30% in cirrhotic subjects compared to normal subjects. A large degree of intersubject variability was noted. Three patients with more severe cirrhosis had a more substantial decrease in venlafaxine clearance (about 90%) compared to normal subjects.

In a second study, venlafaxine was administered orally and intravenously in normal (n = 21) subjects, and in Child-Pugh A (n = 8) and Child-Pugh B (n = 11) subjects (mildly and moderately impaired, respectively). Venlafaxine oral bioavailability was increased 2 to 3 fold; oral elimination half-life was approximately twice as long and oral clearance was reduced by more than half, compared to normal subjects. In hepatically impaired subjects, ODV oral elimination half-life was prolonged by about 40%, while oral clearance for ODV was similar to that for normal subjects. A large degree of intersubject variability was noted.

Dosage adjustment is necessary in these hepatically impaired patients (see DOSAGE AND ADMINISTRATION).

Renal Disease: In a renal impairment study, venlafaxine elimination half-life after oral administration was prolonged by about 50% and clearance was reduced by about 24% in renally impaired patients (GFR=10 to 70 mL/min), compared to normal subjects. In dialysis patients, venlafaxine elimination half-life was prolonged by about 180% and clearance was reduced by about 57% compared to normal subjects. Similarly, ODV elimination half-life was prolonged by about 40% although clearance was unchanged in patients with renal impairment (GFR=10 to 70 mL/min) compared to normal subjects. In dialysis patients, ODV elimination half-life was prolonged by about 142% and clearance was reduced by about 56% compared to normal subjects. A large degree of intersubject variability was noted. Dosage adjustment is necessary in these patients (see DOSAGE AND ADMINISTRATION).

Clinical TrialsMajor Depressive Disorder

The efficacy of venlafaxine hydrochloride extended-release capsules as a treatment for major depressive disorder was established in two placebo-controlled, short-term, flexible-dose studies in adult outpatients meeting DSM-III-R or DSM-IV criteria for major depressive disorder.

A 12-week study utilizing venlafaxine hydrochloride extended-release capsules doses in a range 75 to 150 mg/day (mean dose for completers was 136 mg/day) and an 8-week study utilizing venlafaxine hydrochloride extended-release capsule doses in a range 75 to 225 mg/day (mean dose for completers was 177 mg/day) both demonstrated superiority of venlafaxine hydrochloride extended-release capsule over placebo on the HAM-D total score, HAM-D Depressed Mood Item, the MADRS total score, the Clinical Global Impressions (CGI) Severity of Illness item, and the CGI Global Improvement item. In both studies, venlafaxine hydrochloride extended-release capsules were also significantly better than placebo for certain factors of the HAM-D, including the anxiety/somatization factor, the cognitive disturbance factor, and the retardation factor, as well as for the psychic anxiety score.

A 4-week study of inpatients meeting DSM-III-R criteria for major depressive disorder with melancholia utilizing venlafaxine hydrochloride tablets (immediate release) in a range of 150 to 375 mg/day (t.i.d. schedule) demonstrated superiority of venlafaxine hydrochloride tablets over placebo. The mean dose in completers was 350 mg/day.

Examination of gender subsets of the population studied did not reveal any differential responsiveness on the basis of gender.

In one longer-term study, adult outpatients meeting DSM-IV criteria for major depressive disorder who had responded during an 8-week open trial on venlafaxine hydrochloride extended-release capsules (75, 150, or 225 mg, qAM) were randomized to continuation of their same venlafaxine hydrochloride extended-release capsule dose or to placebo, for up to 26 weeks of observation for relapse. Response during the open phase was defined as a CGI Severity of Illness item score of ≤3 and a HAM-D-21 total score of ≤10 at the day 56 evaluation. Relapse during the double-blind phase was defined as follows: (1) a reappearance of major depressive disorder as defined by DSM-IV criteria and a CGI Severity of Illness item score of ≥4 (moderately ill), (2) 2 consecutive CGI Severity of Illness item scores of ≥4, or (3) a final CGI Severity of Illness item score of ≥4 for any patient who withdrew from the study for any reason. Patients receiving continued venlafaxine hydrochloride extended-release capsules treatment experienced significantly lower relapse rates over the subsequent 26 weeks compared with those receiving placebo.

In a second longer-term trial, adult outpatients meeting DSM-III-R criteria for major depressive disorder, recurrent type, who had responded (HAM-D-21 total score ≤12 at the day 56 evaluation) and continued to be improved [defined as the following criteria being met for days 56 through 180: (1) no HAM-D-21 total score ≥20; (2) no more than 2 HAM-D-21 total scores >10, and (3) no single CGI Severity of Illness item score ≥4 (moderately ill)] during an initial 26 weeks of treatment on venlafaxine hydrochloride tablets (immediate release) [100 to 200 mg/day, on a b.i.d. schedule] were randomized to continuation of their same venlafaxine hydrochloride tablet dose or to placebo. The follow-up period to observe patients for relapse, defined as a CGI Severity of Illness item score ≥4, was for up to 52 weeks. Patients receiving continued venlafaxine hydrochloride tablet treatment experienced significantly lower relapse rates over the subsequent 52 weeks compared with those receiving placebo.

Generalized Anxiety Disorder

The efficacy of venlafaxine hydrochloride extended-release capsules as a treatment for Generalized Anxiety Disorder (GAD) was established in two 8-week, placebo-controlled, fixed-dose studies, one 6-month, placebo-controlled, fixed-dose study, and one 6-month, placebo-controlled, flexible-dose study in adult outpatients meeting DSM-IV criteria for GAD.

One 8-week study evaluating venlafaxine hydrochloride extended-release capsules doses of 75, 150, and 225 mg/day, and placebo showed that the 225 mg/day dose was more effective than placebo on the Hamilton Rating Scale for Anxiety (HAM-A) total score, both the HAM-A anxiety and tension items, and the Clinical Global Impressions (CGI) scale. While there was also evidence for superiority over placebo for the 75 and 150 mg/day doses, these doses were not as consistently effective as the highest dose. A second 8-week study evaluating venlafaxine hydrochloride extended-release capsules doses of 75 and 150 mg/day and placebo showed that both doses were more effective than placebo on some of these same outcomes; however, the 75 mg/day dose was more consistently effective than the 150 mg/day dose. A dose-response relationship for effectiveness in GAD was not clearly established in the 75 to 225 mg/day dose range utilized in these two studies.

Two 6-month studies, one evaluating venlafaxine hydrochloride extended-release capsules doses of 37.5, 75, and 150 mg/day and the other evaluating venlafaxine hydrochloride extended-release capsules doses of 75 to 225 mg/day, showed that daily doses of 75 mg or higher were more effective than placebo on the HAM-A total, both the HAM-A anxiety and tension items, and the CGI scale during 6 months of treatment. While there was also evidence for superiority over placebo for the 37.5 mg/day dose, this dose was not as consistently effective as the higher doses.

Examination of gender subsets of the population studied did not reveal any differential responsiveness on the basis of gender.

Social Anxiety Disorder (Social Phobia)

The efficacy of venlafaxine hydrochloride extended-release capsules as a treatment for Social Anxiety Disorder (also known as Social Phobia) was established in four double-blind, parallel-group, 12-week, multicenter, placebo-controlled, flexible-dose studies and one double-blind, parallel-group, 6-month, placebo-controlled, fixed/flexible-dose study in adult outpatients meeting DSM-IV criteria for Social Anxiety Disorder. Patients received doses in a range of 75 to 225 mg/day. Efficacy was assessed with the Liebowitz Social Anxiety Scale (LSAS). In these five trials, venlafaxine hydrochloride extended-release capsules were significantly more effective than placebo on change from baseline to endpoint on the LSAS total score. There was no evidence for any greater effectiveness of the 150 to 225 mg/day group compared to the 75 mg/day group in the 6-month study.

Examination of subsets of the population studied did not reveal any differential responsiveness on the basis of gender. There was insufficient information to determine the effect of age or race on outcome in these studies.

Panic Disorder

The efficacy of venlafaxine hydrochloride extended-release capsules as a treatment for panic disorder was established in two double-blind, 12-week, multicenter, placebo-controlled studies in adult outpatients meeting DSM-IV criteria for panic disorder, with or without agoraphobia. Patients received fixed doses of 75 or 150 mg/day in one study and 75 or 225 mg/day in the other study.

Efficacy was assessed on the basis of outcomes in three variables: (1) percentage of patients free of full-symptom panic attacks on the Panic and Anticipatory Anxiety Scale (PAAS); (2) mean change from baseline to endpoint on the Panic Disorder Severity Scale (PDSS) total score; and (3) percentage of patients rated as responders (much improved or very much improved) on the Clinical Global Impressions (CGI) Improvement scale. In these two trials, venlafaxine hydrochloride extended-release capsules were significantly more effective than placebo in all three variables.

In the two 12-week studies described above, one evaluating venlafaxine hydrochloride extended-release capsule doses of 75 and 150 mg/day and the other evaluating venlafaxine hydrochloride extended-release capsule doses of 75 and 225 mg/day, efficacy was established for each dose. A dose-response relationship for effectiveness in patients with panic disorder was not clearly established in fixed-dose studies.

Examination of subsets of the population studied did not reveal any differential responsiveness on the basis of gender. There was insufficient information to determine the effect of age or race on outcome in these studies.

In a longer-term study, adult outpatients meeting DSM-IV criteria for panic disorder who had responded during a 12-week open phase with venlafaxine hydrochloride extended-release capsules (75 to 225 mg/day) were randomly assigned to continue the same venlafaxine hydrochloride extended-release capsule dose (75, 150, or 225 mg) or switch to placebo for observation for relapse under double-blind conditions. Response during the open phase was defined as ≤ 1 full-symptom panic attack per week during the last 2 weeks of the open phase and a CGI Improvement score of 1 (very much improved) or 2 (much improved). Relapse during the double-blind phase was defined as having 2 or more full-symptom panic attacks per week for 2 consecutive weeks or having discontinued due to loss of effectiveness as determined by the investigators during the study. Randomized patients were in response status for a mean time of 34 days prior to being randomized. In the randomized phase following the 12-week open-label period, patients receiving continued venlafaxine hydrochloride extended-release capsules experienced a significantly longer time to relapse.

INDICATIONS & USAGE SECTION

Major Depressive Disorder

Venlafaxine hydrochloride extended-release capsules are indicated for the treatment of major depressive disorder.

The efficacy of venlafaxine hydrochloride extended-release capsules in the treatment of major depressive disorder was established in 8- and 12-week controlled trials of adult outpatients whose diagnoses corresponded most closely to the DSM-III-R or DSM-IV category of major depressive disorder (see Clinical Trials).

A major depressive episode (DSM-IV) implies a prominent and relatively persistent (nearly every day for at least 2 weeks) depressed mood or the loss of interest or pleasure in nearly all activities, representing a change from previous functioning, and includes the presence of at least five of the following nine symptoms during the same two-week period: depressed mood, markedly diminished interest or pleasure in usual activities, significant change in weight and/or appetite, insomnia or hypersomnia, psychomotor agitation or retardation, increased fatigue, feelings of guilt or worthlessness, slowed thinking or impaired concentration, a suicide attempt or suicidal ideation.

The efficacy of venlafaxine hydrochloride tablets (immediate release) in the treatment of major depressive disorder in adult inpatients meeting diagnostic criteria for major depressive disorder with melancholia was established in a 4-week controlled trial (see Clinical Trials). The safety and efficacy of venlafaxine hydrochloride extended-release capsules in hospitalized depressed patients have not been adequately studied.

The efficacy of venlafaxine hydrochloride extended-release capsules in maintaining a response in major depressive disorder for up to 26 weeks following 8 weeks of acute treatment was demonstrated in a placebo-controlled trial. The efficacy of venlafaxine hydrochloride extended-release tablets (immediate release) in maintaining a response in patients with recurrent major depressive disorder who had responded and continued to be improved during an initial 26 weeks of treatment and were then followed for a period of up to 52 weeks was demonstrated in a second placebo-controlled trial (see Clinical Trials). Nevertheless, the physician who elects to use venlafaxine hydrochloride tablets/venlafaxine hydrochloride extended-release capsules for extended periods should periodically re-evaluate the long-term usefulness of the drug for the individual patient (see DOSAGE AND ADMINISTRATION).

Generalized Anxiety Disorder

Venlafaxine hydrochloride extended-release capsules are indicated for the treatment of Generalized Anxiety Disorder (GAD) as defined in DSM-IV. Anxiety or tension associated with the stress of everyday life usually does not require treatment with an anxiolytic.

The efficacy of venlafaxine hydrochloride extended-release capsules in the treatment of GAD was established in 8-week and 6-month placebo-controlled trials in adult outpatients diagnosed with GAD according to DSM-IV criteria (see Clinical Trials).

Generalized Anxiety Disorder (DSM-IV) is characterized by excessive anxiety and worry (apprehensive expectation) that is persistent for at least 6 months and which the person finds difficult to control. It must be associated with at least 3 of the following 6 symptoms: restlessness or feeling keyed up or on edge, being easily fatigued, difficulty concentrating or mind going blank, irritability, muscle tension, sleep disturbance.

Although the effectiveness of venlafaxine hydrochloride extended-release capsules have been demonstrated in 6-month clinical trials in patients with GAD, the physician who elects to use venlafaxine hydrochloride extended-release capsules for extended periods should periodically re-evaluate the long-term usefulness of the drug for the individual patient (see DOSAGE AND ADMINISTRATION).

Social Anxiety Disorder

Venlafaxine hydrochloride extended-release capsules is indicated for the treatment of Social Anxiety Disorder, also known as Social Phobia, as defined in DSM-IV (300.23).

Social Anxiety Disorder (DSM-IV) is characterized by a marked and persistent fear of 1 or more social or performance situations in which the person is exposed to unfamiliar people or to possible scrutiny by others. Exposure to the feared situation almost invariably provokes anxiety, which may approach the intensity of a panic attack. The feared situations are avoided or endured with intense anxiety or distress. The avoidance, anxious anticipation, or distress in the feared situation(s) interferes significantly with the person's normal routine, occupational or academic functioning, or social activities or relationships, or there is a marked distress about having the phobias. Lesser degrees of performance anxiety or shyness generally do not require psychopharmacological treatment.

The efficacy of venlafaxine hydrochloride extended-release capsules in the treatment of Social Anxiety Disorder was established in four 12-week and one 6-month placebo-controlled trials in adult outpatients with Social Anxiety Disorder (DSM-IV) (see Clinical Trials).

Although the effectiveness of venlafaxine hydrochloride extended-release capsules have been demonstrated in a 6-month clinical trial in patients with Social Anxiety Disorder, the physician who elects to use venlafaxine hydrochloride extended-release capsules for extended periods should periodically re-evaluate the long-term usefulness of the drug for the individual patient (see DOSAGE AND ADMINISTRATION).

Panic Disorder

Venlafaxine hydrochloride extended-release capsules are indicated for the treatment of panic disorder, with or without agoraphobia, as defined in DSM-IV. Panic disorder is characterized by the occurrence of unexpected panic attacks and associated concern about having additional attacks, worry about the implications or consequences of the attacks, and/or a significant change in behavior related to the attacks.

Panic disorder (DSM-IV) is characterized by recurrent, unexpected panic attacks, i.e., a discrete period of intense fear or discomfort, in which four (or more) of the following symptoms develop abruptly and reach a peak within 10 minutes: 1) palpitations, pounding heart, or accelerated heart rate; 2) sweating; 3) trembling or shaking; 4) sensations of shortness of breath or smothering; 5) feeling of choking; 6) chest pain or discomfort; 7) nausea or abdominal distress; 8) feeling dizzy, unsteady, lightheaded, or faint; 9) derealization (feelings of unreality) or depersonalization (being detached from oneself); 10) fear of losing control; 11) fear of dying; 12) paresthesias (numbness or tingling sensations); 13) chills or hot flushes.

The efficacy of venlafaxine hydrochloride extended-release capsules in the treatment of panic disorder was established in two 12-week placebo-controlled trials in adult outpatients with panic disorder (DSM-IV). The efficacy of venlafaxine hydrochloride extended-release capsules in prolonging time to relapse in panic disorder among responders following 12 weeks of open-label acute treatment was demonstrated in a placebo-controlled study (see CLINICAL PHARMACOLOGY, Clinical Trials). Nevertheless, the physician who elects to use venlafaxine hydrochloride extended-release capsules for extended periods should periodically re-evaluate the long-term usefulness of the drug for the individual patient (see DOSAGE AND ADMINISTRATION).

CONTRAINDICATIONS SECTION

CONTRAINDICATIONS

Hypersensitivity to venlafaxine hydrochloride or to any excipients in the formulation.

The use of MAOIs intended to treat psychiatric disorders with venlafaxine hydrochloride extended-release capsules or within 7 days of stopping treatment with venlafaxine hydrochloride extended-release capsules is contraindicated because of an increased risk of serotonin syndrome. The use of venlafaxine hydrochloride extended-release capsules within 14 days of stopping an MAOI intended to treat psychiatric disorders is also contraindicated (see WARNINGS and DOSAGE AND ADMINISTRATION).

Starting venlafaxine hydrochloride extended-release capsules in a patient who is being treated with MAOIs such as linezolid or intravenous methylene blue is also contraindicated because of an increased risk of serotonin syndrome (see WARNINGS and DOSAGE AND ADMINISTRATION).

WARNINGS SECTION

Clinical Worsening and Suicide Risk

Patients with major depressive disorder (MDD), both adult and pediatric, may experience worsening of their depression and/or the emergence of suicidal ideation and behavior (suicidality) or unusual changes in behavior, whether or not they are taking antidepressant medications, and this risk may persist until significant remission occurs. Suicide is a known risk of depression and certain other psychiatric disorders, and these disorders themselves are the strongest predictors of suicide. There has been a long standing concern, however, that antidepressants may have a role in inducing worsening of depression and the emergence of suicidality in certain patients during the early phases of treatment. Pooled analyses of short-term placebo-controlled trials of antidepressant drugs (SSRIs and others) showed that these drugs increase the risk of suicidal thinking and behavior (suicidality) in children, adolescents, and young adults (ages 18 to 24) with major depressive disorder (MDD) and other psychiatric disorders. Short-term studies did not show an increase in the risk of suicidality with antidepressants compared to placebo in adults beyond age 24; there was a reduction with antidepressants compared to placebo in adults aged 65 and older.

The pooled analyses of placebo-controlled trials in children and adolescents with MDD, obsessive compulsive disorder (OCD), or other psychiatric disorders included a total of 24 short-term trials of 9 antidepressant drugs in over 4400 patients. The pooled analyses of placebo-controlled trials in adults with MDD or other psychiatric disorders included a total of 295 short-term trials (median duration of 2 months) of 11 antidepressant drugs in over 77,000 patients. There was considerable variation in risk of suicidality among drugs, but a tendency toward an increase in the younger patients for almost all drugs studied. There were differences in absolute risk of suicidality across the different indications, with the highest incidence in MDD. The risk differences (drug vs placebo), however, were relatively stable within age strata and across indications. These risk differences (drug-placebo difference in the number of cases of suicidality per 1000 patients treated) are provided in Table 1.

Table 1
Age Range | Drug-Placebo Difference in Number of Cases of Suicidality per 1000 Patients Treated
 | Increases Compared to Placebo
<18 | 14 additional cases
18-24 | 5 additional cases
 | Decreases Compared to Placebo
25 to 64 | 1 fewer case
≥65 | 6 fewer cases

No suicides occurred in any of the pediatric trials. There were suicides in the adult trials, but the number was not sufficient to reach any conclusion about drug effect on suicide.

It is unknown whether the suicidality risk extends to longer-term use, i.e., beyond several months. However, there is substantial evidence from placebo-controlled maintenance trials in adults with depression that the use of antidepressants can delay the recurrence of depression.

All patients being treated with antidepressants for any indication should be monitored appropriately and observed closely for clinical worsening, suicidality, and unusual changes in behavior, especially during the initial few months of a course of drug therapy, or at times of dose changes, either increases or decreases.

The following symptoms, anxiety, agitation, panic attacks, insomnia, irritability, hostility, aggressiveness, impulsivity, akathisia (psychomotor restlessness), hypomania, and mania, have been reported in adult and pediatric patients being treated with antidepressants for major depressive disorder as well as for other indications, both psychiatric and nonpsychiatric. Although a causal link between the emergence of such symptoms and either the worsening of depression and/or the emergence of suicidal impulses has not been established, there is concern that such symptoms may represent precursors to emerging suicidality.

Consideration should be given to changing the therapeutic regimen, including possibly discontinuing the medication, in patients whose depression is persistently worse, or who are experiencing emergent suicidality or symptoms that might be precursors to worsening depression or suicidality, especially if these symptoms are severe, abrupt in onset, or were not part of the patient's presenting symptoms.

If the decision has been made to discontinue treatment, medication should be tapered, as rapidly as is feasible, but with recognition that abrupt discontinuation can be associated with certain symptoms (see PRECAUTIONS and DOSAGE AND ADMINISTRATION, Discontinuation of Treatment with Venlafaxine Hydrochloride Extended-Release Capsules, for a description of the risks of discontinuation of venlafaxine hydrochloride extended-release capsules).

Families and caregivers of patients being treated with antidepressants for major depressive disorder or other indications, both psychiatric and nonpsychiatric, should be alerted about the need to monitor patients for the emergence of agitation, irritability, unusual changes in behavior, and the other symptoms described above, as well as the emergence of suicidality, and to report such symptoms immediately to health care providers. Such monitoring should include daily observation by families and caregivers. Prescriptions for venlafaxine hydrochloride extended-release capsules should be written for the smallest quantity of capsules consistent with good patient management, in order to reduce the risk of overdose.

Screening Patients for Bipolar Disorder

A major depressive episode may be the initial presentation of bipolar disorder. It is generally believed (though not established in controlled trials) that treating such an episode with an antidepressant alone may increase the likelihood of precipitation of a mixed/manic episode in patients at risk for bipolar disorder. Whether any of the symptoms described above represent such a conversion is unknown. However, prior to initiating treatment with an antidepressant, patients with depressive symptoms should be adequately screened to determine if they are at risk for bipolar disorder; such screening should include a detailed psychiatric history, including a family history of suicide, bipolar disorder, and depression. It should be noted that venlafaxine hydrochloride extended-release capsules are not approved for use in treating bipolar depression.

Serotonin Syndrome

The development of a potentially life-threatening serotonin syndrome has been reported with SNRIs and SSRIs, including venlafaxine hydrochloride extended-release capsules, alone but particularly with concomitant use of other serotonergic drugs (including triptans, tricyclic antidepressants, fentanyl, lithium, tramadol, tryptophan, buspirone, and St. John's Wort) and with drugs that impair metabolism of serotonin (in particular, MAOIs, both those intended to treat psychiatric disorders and also others, such as linezolid and intravenous methylene blue).

Serotonin syndrome symptoms may include mental status changes (e.g., agitation, hallucinations, delirium, and coma), autonomic instability (e.g., tachycardia, labile blood pressure, dizziness, diaphoresis, flushing, hyperthermia), neuromuscular symptoms (e.g., tremor, rigidity, myoclonus, hyperreflexia, incoordination), seizures, and/or gastrointestinal symptoms (e.g., nausea, vomiting, diarrhea). Patients should be monitored for the emergence of serotonin syndrome.

The concomitant use of venlafaxine hydrochloride extended-release capsules with MAOIs intended to treat psychiatric disorders is contraindicated. Venlafaxine hydrochloride extended-release capsules should also not be started in a patient who is being treated with MAOIs such as linezolid or intravenous methylene blue. All reports with methylene blue that provided information on the route of administration involved intravenous administration in the dose range of 1 mg/kg to 8 mg/kg. No reports involved the administration of methylene blue by other routes (such as oral tablets or local tissue injection) or at lower doses. There may be circumstances when it is necessary to initiate treatment with a MAOI such as linezoid or intravenous methylene blue in a patient taking venlafaxine hydrochloride extended-release capsules. Venlafaxine hydrochloride extended-release capsules should be discontinued before initiating treatment with the MAOI (see CONTRAINDICATIONS and DOSAGE AND ADMINISTRATION).

If concomitant use of venlafaxine hydrochloride extended-release capsules with other serotonergic drugs, including triptans, tricyclic antidepressants, fentanyl, lithium, tramadol, buspirone, tryptophan, and St. John's Wort is clinically warranted, patients should be made aware of a potential increased risk for serotonin syndrome, particularly during treatment initiation and dose increases.

Treatment with venlafaxine hydrochloride extended-release capsules and any concomitant serotonergic agents should be discontinued immediately if the above events occur and supportive symptomatic treatment should be initiated.

Angle-Closure Glaucoma

The pupillary dilation that occurs following use of many antidepressant drugs including venlafaxine hydrochloride may trigger an angle closure attack in a patient with anatomically narrow angles who does not have a patent iridectomy.

Sustained Hypertension

Venlafaxine hydrochloride extended-release capsule treatment is associated with sustained hypertension (defined as treatment-emergent supine diastolic blood pressure (SDBP) ≥90 mm Hg and ≥10 mm Hg above baseline for 3 consecutive on-therapy visits (see Table 2).

An analysis for patients in venlafaxine hydrochloride tablet (immediate release) studies meeting criteria for sustained hypertension revealed a dose-dependent increase in the incidence of sustained hypertension for venlafaxine hydrochloride tablets (immediate release) (see Table 3).

An insufficient number of patients received mean doses of venlafaxine hydrochloride extended-release capsules over 300 mg/day to fully evaluate the incidence of sustained increases in blood pressure at these higher doses.

Table 2 Number (%) of Sustained Elevations in SDBP in Venlafaxine Hydrochloride Extended-Release Capsules Premarketing Studies by Indication
MDD (75-375 mg/day) | GAD (37.5-225 mg/day) | Social Anxiety Disorder (75-225 mg/day) | Panic Disorder (75-225 mg/day)
19/705 (3) | 5/1011 (0.5) | 5/771 (0.6) | 9/973 (0.9)
MDD = major depressive disorder
GAD = generalized anxiety disorder

Table 3 Incidence (%) of Sustained Elevations in SDBP in Venlafaxine Hydrochloride Tablet Immediate Release Studies
Venlafaxine hydrochloride mg/day | Incidence
<100 | 3%
>100 to ≤200 | 5%
>200 to ≤300 | 7%
>300 | 13%

In premarketing major depressive disorder studies, 0.7% (5/705) of the venlafaxine hydrochloride extended-release capsule-treated patients discontinued treatment because of elevated blood pressure. Among these patients, most of the blood pressure increases were in a modest range (12 to 16 mm Hg, SDBP). In premarketing GAD studies up to 8 weeks and up to 6 months, 0.7% (10/1381) and 1.3% (7/535) of the venlafaxine hydrochloride extended-release capsule-treated patients, respectively, discontinued treatment because of elevated blood pressure. Among these patients, most of the blood pressure increases were in a modest range (12 to 25 mm Hg, SDBP up to 8 weeks; 8 to 28 mm Hg up to 6 months). In premarketing Social Anxiety Disorder studies up to 6 months, 0.6% (5/771) of the venlafaxine hydrochloride extended-release capsule-treated patients discontinued treatment because of elevated blood pressure. In these patients, the blood pressure increases were modest (1-24 mm Hg, SDBP). In premarketing panic disorder studies up to 12 weeks, 0.5% (5/1001) of the venlafaxine hydrochloride extended-release capsule-treated patients discontinued treatment because of elevated blood pressure. In these patients, the blood pressure increases were in a modest range (7 to 19 mm Hg, SDBP).

Sustained increases of SDBP could have adverse consequences. Cases of elevated blood pressure requiring immediate treatment have been reported in post marketing experience. Pre-existing hypertension should be controlled before treatment with venlafaxine. It is recommended that patients receiving venlafaxine hydrochloride extended-release capsules have regular monitoring of blood pressure. For patients who experience a sustained increase in blood pressure while receiving venlafaxine, either dose reduction or discontinuation should be considered.

Elevations in Systolic and Diastolic Blood Pressure

In placebo-controlled premarketing studies, there were changes in mean blood pressure (see Table 4 for mean changes in supine systolic and supine diastolic blood pressure). Across most indications, a dose-related increase in supine systolic and diastolic blood pressure was evident in venlafaxine hydrochloride extended-release capsule-treated patients.

Table 4 Final On-Therapy Mean Changes from Baseline in Supine Systolic and Diastolic Blood Pressure (mm Hg) Results by Indication, Study Duration, and Dose in Placebo-Controlled Trials
 | Venlafaxine hydrochloride extended-release Capsules mg/day | Placebo
 | ≤75 | >75
 | SSBP * | SDBP † | SSBP | SDBP | SSBP | SDBP
Major Depressive Disorder
8-12 weeks | -0.28 | 0.37 | 2.93 | 3.56 | -1.08 | -0.10
Generalized Anxiety Disorder
8 weeks | -0.28 | 0.02 | 2.40 | 1.68 | -1.26 | -0.92
6 months | 1.27 | -0.69 | 2.06 | 1.28 | -1.29 | -0.74
Social Anxiety Disorder
12 weeks | -0.29 | -1.26 | 1.18 | 1.34 | -1.96 | -1.22
6 months | -0.98 | -0.49 | 2.51 | 1.96 | -1.84 | -0.65
Panic Disorder
10-12 weeks | -1.15 | 0.97 | -0.36 | 0.16 | -1.29 | -0.99
*Supine Systolic Blood Pressure †Supine Diastolic Blood Pressure

Across all clinical trials in MDD, GAD, Social Anxiety Disorder and panic disorder, 1.4% of patients in the venlafaxine hydrochloride extended-release capsule-treated groups experienced a ≥15 mm Hg increase in supine diastolic blood pressure with blood pressure ≥105 mm Hg compared to 0.9% of patients in the placebo groups. Similarly, 1% of patients in the venlafaxine hydrochloride extended-release capsule-treated groups experienced a ≥20 mm Hg increase in supine systolic blood pressure with blood pressure ≥180 mm Hg compared to 0.3% of patients in the placebo groups

PRECAUTIONS SECTION

GeneralDiscontinuation of Treatment with venlafaxine hydrochloride extended-release capsules

Discontinuation symptoms have been systematically evaluated in patients taking venlafaxine, to include prospective analyses of clinical trials in Generalized Anxiety Disorder and retrospective surveys of trials in major depressive disorder, and Social Anxiety Disorder. Abrupt discontinuation or dose reduction of venlafaxine at various doses has been found to be associated with the appearance of new symptoms, the frequency of which increased with increased dose level and with longer duration of treatment. Reported symptoms include agitation, anorexia, anxiety, confusion, impaired coordination and balance, diarrhea, dizziness, dry mouth, dysphoric mood, fasciculation, fatigue, flu-like symptoms, headaches, hypomania, insomnia, nausea, nervousness, nightmares, sensory disturbances (including shock-like electrical sensations), somnolence, sweating, tremor, vertigo, and vomiting.

During marketing of venlafaxine hydrochloride extended-release capsules, other SNRIs (Serotonin and Norepinephrine Reuptake Inhibitors), and SSRIs (Selective Serotonin Reuptake Inhibitors), there have been spontaneous reports of adverse events occurring upon discontinuation of these drugs, particularly when abrupt, including the following: dysphoric mood, irritability, agitation, dizziness, sensory disturbances (e.g. paresthesias such as electric shock sensations), anxiety, confusion, headache, lethargy, emotional lability, insomnia, hypomania, tinnitus, and seizures. While these events are generally self-limiting, there have been reports of serious discontinuation symptoms.

Patients should be monitored for these symptoms when discontinuing treatment with venlafaxine hydrochloride extended-release capsules. A gradual reduction in the dose rather than abrupt cessation is recommended whenever possible. If intolerable symptoms occur following a decrease in the dose or upon discontinuation of treatment, then resuming the previously prescribed dose may be considered. Subsequently, the physician may continue decreasing the dose but at a more gradual rate (see DOSAGE AND ADMINISTRATION).

Insomnia and Nervousness

Treatment-emergent insomnia and nervousness were more commonly reported for patients treated with venlafaxine hydrochloride extended-release capsules than with placebo in pooled analyses of short-term major depressive disorder, GAD, Social Anxiety Disorder, and panic disorder studies, as shown in Table 5.

Table 5 Incidence of Insomnia and Nervousness in Placebo-Controlled Major Depressive Disorder, GAD, Social Anxiety Disorder, and Panic Disorder Trials
 | Major Depressive Disorder | GAD | Social Anxiety Disorder | Panic Disorder
Symptom | Venlafaxine hydrochloride extended-release capsules n = 357 | Placebo n = 285 | Venlafaxine hydrochloride extended-release capsules n = 1381 | Placebo n = 555 | Venlafaxine hydrochloride extended-release capsules n = 819 | Placebo n = 695 | Venlafaxine hydrochloride extended-release capsules n = 1001 | Placebo n = 662
Insomnia | 17% | 11% | 15% | 10% | 24% | 8% | 17% | 9%
Nervousness | 10% | 5% | 6% | 4% | 10% | 5% | 4% | 6%

Insomnia and nervousness each led to drug discontinuation in 0.9% of the patients treated with venlafaxine hydrochloride extended-release capsules in major depressive disorder studies.

In GAD trials, insomnia and nervousness led to drug discontinuation in 3% and 2%, respectively, of the patients treated with venlafaxine hydrochloride extended-release capsules up to 8 weeks and 2% and 0.7%, respectively, of the patients treated with venlafaxine hydrochloride extended-release capsules up to 6 months.

In Social Anxiety Disorder trials, insomnia and nervousness led to drug discontinuation in 2% and 1%, respectively, of the patients treated with venlafaxine hydrochloride extended-release capsules up to 12 weeks and 2% and 3% respectively, of the patients treated with venlafaxine hydrochloride extended-release up to 6 months.

In panic disorder trials, insomnia and nervousness led to drug discontinuation in 1% and 0.1%, respectively, of the patients treated with venlafaxine hydrochloride extended-release capsules up to 12 weeks.

Changes in Weight

Adult Patients: A loss of 5% or more of body weight occurred in 7% of venlafaxine hydrochloride extended-release capsule-treated and 2% of placebo-treated patients in the short-term placebo-controlled major depressive disorder trials. The discontinuation rate for weight loss associated with venlafaxine hydrochloride extended-release capsules was 0.1% in major depressive disorder studies. In placebo-controlled GAD studies, a loss of 7% or more of body weight occurred in 3% of venlafaxine hydrochloride extended-release capsules patients and 1% of placebo patients who received treatment for up to 6 months. The discontinuation rate for weight loss was 0.3% for patients receiving venlafaxine hydrochloride extended-release capsules in GAD studies for up to eight weeks. In placebo-controlled Social Anxiety Disorder trials, 4% of the venlafaxine hydrochloride extended-release capsule-treated and 1% of the placebo-treated patients sustained a loss of 7% or more of body weight during up to 6 months of treatment. None of the patients receiving venlafaxine hydrochloride extended-release capsules in Social Anxiety Disorder studies discontinued for weight loss. In placebo-controlled panic disorder trials, 3% of the venlafaxine hydrochloride extended-release capsule-treated and 2% of the placebo-treated patients sustained a loss of 7% or more of body weight during up to 12 weeks of treatment. None of the patients receiving venlafaxine hydrochloride extended-release capsules in panic disorder studies discontinued for weight loss.

The safety and efficacy of venlafaxine therapy in combination with weight loss agents, including phentermine, have not been established. Co-administration of venlafaxine hydrochloride extended-release capsules and weight loss agents is not recommended. Venlafaxine hydrochloride extended-release capsules are not indicated for weight loss alone or in combination with other products.

Pediatric Patients: Weight loss has been observed in pediatric patients (ages 6-17) receiving venlafaxine hydrochloride extended-release capsules. In a pooled analysis of four eight-week, double-blind, placebo-controlled, flexible dose outpatient trials for major depressive disorder (MDD) and generalized anxiety disorder (GAD), venlafaxine hydrochloride extended-release capsule-treated patients lost an average of 0.45 kg (n = 333), while placebo-treated patients gained an average of 0.77 kg (n = 333). More patients treated with venlafaxine hydrochloride extended-release capsules than with placebo experienced a weight loss of at least 3.5% in both the MDD and the GAD studies (18% of venlafaxine hydrochloride extended-release capsule-treated patients vs. 3.6% of placebo-treated patients; p<0.001). In a 16-week, double-blind, placebo-controlled, flexible dose outpatient trial for Social Anxiety Disorder, venlafaxine hydrochloride extended-release capsule-treated patients lost an average of 0.75 kg (n = 137), while placebo-treated patients gained an average of 0.76 kg (n = 148). More patients treated with venlafaxine hydrochloride extended-release capsules than with placebo experienced a weight loss of at least 3.5% in the Social Anxiety Disorder study (47% of venlafaxine hydrochloride extended-release capsules-treated patients vs. 14% of placebo-treated patients; p<0.001). Weight loss was not limited to patients with treatment-emergent anorexia (see PRECAUTIONS, General, Changes in Appetite).

The risks associated with longer-term venlafaxine hydrochloride extended-release capsules use were assessed in an open-label MDD study of children and adolescents who received venlafaxine hydrochloride extended-release capsules for up to six months. The children and adolescents in the study had increases in weight that were less than expected based on data from age- and sex-matched peers. The difference between observed weight gain and expected weight gain was larger for children (<12 years old) than for adolescents (≥12 years old).

Changes in Height

Pediatric Patients: During the eight-week, placebo-controlled GAD studies, venlafaxine hydrochloride extended-release capsule-treated patients (ages 6-17) grew an average of 0.3 cm (n = 122), while placebo-treated patients grew an average of 1.0 cm (n = 132); p=0.041. This difference in height increase was most notable in patients younger than twelve. During the eight-week placebo-controlled MDD studies, venlafaxine hydrochloride extended-release capsule-treated patients grew an average of 0.8 cm (n = 146), while placebo-treated patients grew an average of 0.7 cm (n = 147). During the 16-week, placebo-controlled Social Anxiety Disorder study, both the venlafaxine hydrochloride extended-release capsule-treated (n = 109) and the placebo-treated (n = 112) patients each grew an average of 1.0 cm. In the six-month, open-label MDD study, children and adolescents had height increases that were less than expected based on data from age- and sex-matched peers. The difference between observed growth rates and expected growth rates was larger for children (<12 years old) than for adolescents (≥12 years old).

Changes in Appetite

Adult Patients: Treatment-emergent anorexia was more commonly reported for venlafaxine hydrochloride extended-release capsule-treated (8%) than placebo-treated patients (4%) in the pool of short-term, double-blind, placebo-controlled major depressive disorder studies. The discontinuation rate for anorexia associated with venlafaxine hydrochloride extended-release capsules was 1.0% in major depressive disorder studies. Treatment-emergent anorexia was more commonly reported for venlafaxine hydrochloride extended-release capsule-treated (8%) than placebo-treated patients (2%) in the pool of short-term, double-blind, placebo-controlled GAD studies. The discontinuation rate for anorexia was 0.9% for patients receiving venlafaxine hydrochloride extended-release capsules for up to 8 weeks in GAD studies. Treatment-emergent anorexia was more commonly reported for venlafaxine hydrochloride extended-release capsule-treated (17%) than placebo-treated patients (2%) in the pool of short-term, double-blind, placebo-controlled Social Anxiety Disorder studies. The discontinuation rate for anorexia was 0.6% for patients receiving venlafaxine hydrochloride extended-release capsules for up to 12 weeks in Social Anxiety Disorder studies; no patients discontinued for anorexia between week 12 and month 6. Treatment-emergent anorexia was more commonly reported for venlafaxine hydrochloride extended-release capsule-treated (8%) than placebo-treated patients (3%) in the pool of short-term, double-blind, placebo-controlled panic disorder studies. The discontinuation rate for anorexia was 0.4% for patients receiving venlafaxine hydrochloride extended-release capsules for up to 12 weeks in panic disorder studies.

Pediatric Patients: Decreased appetite has been observed in pediatric patients receiving venlafaxine hydrochloride extended-release capsules. In the placebo-controlled trials for GAD and MDD, 10% of patients aged 6-17 treated with venlafaxine hydrochloride extended-release capsules for up to eight weeks and 3% of patients treated with placebo reported treatment-emergent anorexia (decreased appetite). None of the patients receiving venlafaxine hydrochloride extended-release capsules discontinued for anorexia or weight loss. In the placebo-controlled trial for Social Anxiety Disorder, 22% and 3% of patients aged 8-17 treated for up to 16 weeks with venlafaxine hydrochloride extended-release capsules and placebo, respectively, reported treatment-emergent anorexia (decreased appetite). The discontinuation rates for anorexia were 0.7% and 0.0% for patients receiving venlafaxine hydrochloride extended-release capsules and placebo, respectively; the discontinuation rates for weight loss were 0.7% for patients receiving either venlafaxine hydrochloride extended-release capsules or placebo.

Activation of Mania/Hypomania

During premarketing major depressive disorder studies, mania or hypomania occurred in 0.3% of venlafaxine hydrochloride extended-release capsule-treated patients and no placebo patients. In premarketing GAD studies, no venlafaxine hydrochloride extended-release capsule-treated patients and 0.2% of placebo-treated patients experienced mania or hypomania. In premarketing Social Anxiety Disorder studies, 0.2% venlafaxine hydrochloride extended-release capsule-treated patients and no placebo-treated patients experienced mania or hypomania. In premarketing panic disorder studies, 0.1% of venlafaxine hydrochloride extended-release capsule-treated patients and no placebo-treated patients experienced mania or hypomania. In all premarketing major depressive disorder trials with venlafaxine hydrochloride tablets (immediate release), mania or hypomania occurred in 0.5% of venlafaxine-treated patients compared with no placebo patients. Mania/hypomania has also been reported in a small proportion of patients with mood disorders who were treated with other marketed drugs to treat major depressive disorder. As with all drugs effective in the treatment of major depressive disorder, venlafaxine hydrochloride extended-release capsules should be used cautiously in patients with a history of mania.

Hyponatremia

Hyponatremia may occur as a result of treatment with SSRIs and SNRIs, including venlafaxine hydrochloride extended-release capsules. In many cases, this hyponatremia appears to be the result of the syndrome of inappropriate antidiuretic hormone secretion (SIADH). Cases with serum sodium lower than 110 mmol/L have been reported. Elderly patients may be at greater risk of developing hyponatremia with SSRIs and SNRIs. Also, patients taking diuretics or who are otherwise volume depleted may be at greater risk (see PRECAUTIONS, Geriatric Use). Discontinuation of venlafaxine hydrochloride extended-release capsules should be considered in patients with symptomatic hyponatremia and appropriate medical intervention should be instituted.

Signs and symptoms of hyponatremia include headache, difficulty concentrating, memory impairment, confusion, weakness, and unsteadiness, which may lead to falls. Signs and symptoms associated with more severe and/or acute cases have included hallucination, syncope, seizure, coma, respiratory arrest, and death.

Seizures

During premarketing experience, no seizures occurred among 705 venlafaxine hydrochloride extended-release capsule-treated patients in the major depressive disorder studies, among 1381 venlafaxine hydrochloride extended-release capsule-treated patients in GAD studies, or among 819 venlafaxine hydrochloride extended-release capsule-treated patients in Social Anxiety Disorder studies. In panic disorder studies, 1 seizure occurred among 1,001 venlafaxine hydrochloride extended-release capsule-treated patients. In all premarketing major depressive disorder trials with venlafaxine hydrochloride tablets (immediate release), seizures were reported at various doses in 0.3% (8/3082) of venlafaxine-treated patients. Venlafaxine hydrochloride extended-release capsules, like many antidepressants, should be used cautiously in patients with a history of seizures and should be discontinued in any patient who develops seizures.

Abnormal Bleeding

SSRIs and SNRIs, including venlafaxine hydrochloride extended-release capsules, may increase the risk of bleeding events. ranging from ecchymoses, hematomas, epistaxis, petechiae, and gastrointestinal hemorrhage to life-threatening hemorrhage. Concomitant use of aspirin, nonsteroidal anti-inflammatory drugs, warfarin, and other anti-coagulants or other drugs known to affect platelet function may add to this risk. Case reports and epidemiological studies (case-control and cohort design) have demonstrated an association between use of drugs that interfere with serotonin reuptake and the occurrence of gastrointestinal bleeding.

Patients should be cautioned about the risk of bleeding associated with the concomitant use of venlafaxine hydrochloride extended-release capsules and NSAIDs, aspirin, or other drugs that affect coagulation.

Serum Cholesterol Elevation

Clinically relevant increases in serum cholesterol were recorded in 5.3% of venlafaxine-treated patients and 0.0% of placebo-treated patients treated for at least 3 months in placebo-controlled trials (see ADVERSE REACTIONS-Laboratory Changes). Measurement of serum cholesterol levels should be considered during long-term treatment.

Interstitial Lung Disease and Eosinophilic Pneumonia

Interstitial lung disease and eosinophilic pneumonia associated with venlafaxine therapy have been rarely reported. The possibility of these adverse events should be considered in venlafaxine-treated patients who present with progressive dyspnea, cough or chest discomfort. Such patients should undergo a prompt medical evaluation, and discontinuation of venlafaxine therapy should be considered.

Use in Patients With Concomitant Illness

Premarketing experience with venlafaxine in patients with concomitant systemic illness is limited. Caution is advised in administering venlafaxine hydrochloride extended-release capsules to patients with diseases or conditions that could affect hemodynamic responses or metabolism.

Venlafaxine has not been evaluated or used to any appreciable extent in patients with a recent history of myocardial infarction or unstable heart disease. Patients with these diagnoses were systematically excluded from many clinical studies during venlafaxine's premarketing testing. The electrocardiograms were analyzed for 275 patients who received venlafaxine hydrochloride extended-release capsules and 220 patients who received placebo in 8- to 12-week double-blind, placebo-controlled trials in major depressive disorder, for 610 patients who received venlafaxine hydrochloride extended-release capsules and 298 patients who received placebo in 8-week double-blind, placebo-controlled trials in GAD, for 593 patients who received venlafaxine hydrochloride extended-release capsules and 534 patients who received placebo in 12-week double-blind, placebo-controlled trials in Social Anxiety Disorder, and for 661 patients who received venlafaxine hydrochloride extended-release capsules and 395 patients who received placebo in three 10- to 12-week double-blind, placebo-controlled trials in panic disorder. The mean change from baseline in corrected QT interval (QTc) for venlafaxine hydrochloride extended-release capsule-treated patients in major depressive disorder studies was increased relative to that for placebo-treated patients (increase of 4.7 msec for venlafaxine hydrochloride extended-release capsule and decrease of 1.9 msec for placebo). The mean change from baseline in QTc interval for venlafaxine hydrochloride extended-release capsule-treated patients in the GAD studies did not differ significantly from that with placebo. The mean change from baseline in QTc interval for venlafaxine hydrochloride extended-release capsule-treated patients in the Social Anxiety Disorder studies was increased relative to that for placebo-treated patients (increase of 3.4 msec for venlafaxine hydrochloride extended-release capsules and decrease of 1.6 msec for placebo). The mean change from baseline in QTc interval for venlafaxine hydrochloride extended-release capsule-treated patients in the panic disorder studies was increased relative to that for placebo-treated patients (increase of 1.5 msec for venlafaxine hydrochloride extended-release capsules and decrease of 0.7 msec for placebo).

In these same trials, the mean change from baseline in heart rate for venlafaxine hydrochloride extended-release capsule-treated patients in the major depressive disorder studies was significantly higher than that for placebo (a mean increase of 4 beats per minute for venlafaxine hydrochloride extended-release capsules and 1 beat per minute for placebo). The mean change from baseline in heart rate for venlafaxine hydrochloride extended-release capsule-treated patients in the GAD studies was significantly higher than that for placebo (a mean increase of 3 beats per minute for venlafaxine hydrochloride extended-release capsules and no change for placebo). The mean change from baseline in heart rate for venlafaxine hydrochloride extended-release capsule-treated patients in the Social Anxiety Disorder studies was significantly higher than that for placebo (a mean increase of 5 beats per minute for venlafaxine hydrochloride extended-release capsules and no change for placebo). The mean change from baseline in heart rate for venlafaxine hydrochloride extended-release capsules-treated patients in the panic disorder studies was significantly higher than that for placebo (a mean increase of 3 beats per minute for venlafaxine hydrochloride extended-release capsules and a mean decrease of less than 1 beat per minute for placebo).

In a flexible-dose study, with venlafaxine hydrochloride tablets (immediate release) doses in the range of 200 to 375 mg/day and mean dose greater than 300 mg/day, venlafaxine hydrochloride tablet-treated patients had a mean increase in heart rate of 8.5 beats per minute compared with 1.7 beats per minute in the placebo group.

As increases in heart rate were observed, caution should be exercised in patients whose underlying medical conditions might be compromised by increases in heart rate (eg, patients with hyperthyroidism, heart failure, or recent myocardial infarction).

Evaluation of the electrocardiograms for 769 patients who received venlafaxine hydrochloride tablets (immediate release) in 4- to 6-week double-blind, placebo-controlled trials showed that the incidence of trial-emergent conduction abnormalities did not differ from that with placebo.

In patients with renal impairment (GFR = 10 to 70 mL/min) or cirrhosis of the liver, the clearances of venlafaxine and its active metabolites were decreased, thus prolonging the elimination half-lives of these substances. A lower dose may be necessary (see DOSAGE AND ADMINISTRATION). Venlafaxine hydrochloride extended-release capsules, like all drugs effective in the treatment of major depressive disorder, should be used with caution in such patients.

Information for Patients

Prescribers or other health professionals should inform patients, their families, and their caregivers about the benefits and risks associated with treatment with venlafaxine hydrochloride extended-release capsules and should counsel them in its appropriate use. A patient Medication Guide about “Antidepressant Medicines, Depression and Other Serious Mental Illness, and Suicidal Thoughts or Actions” is available for venlafaxine hydrochloride extended-release capsules. The prescriber or health professional should instruct patients, their families, and their caregivers to read the Medication Guide and should assist them in understanding its contents. Patients should be given the opportunity to discuss the contents of the Medication Guide and to obtain answers to any questions they may have. The complete text of the Medication Guide is reprinted at the end of this document.

Patients should be advised of the following issues and asked to alert their prescriber if these occur while taking venlafaxine hydrochloride extended-release capsules.

Clinical Worsening and Suicide Risk: Patients, their families, and their caregivers should be encouraged to be alert to the emergence of anxiety, agitation, panic attacks, insomnia, irritability, hostility, aggressiveness, impulsivity, akathisia (psychomotor restlessness), hypomania, mania, other unusual changes in behavior, worsening of depression, and suicidal ideation, especially early during antidepressant treatment and when the dose is adjusted up or down. Families and caregivers of patients should be advised to look for the emergence of such symptoms on a day-to-day basis, since changes may be abrupt. Such symptoms should be reported to the patient's prescriber or health professional, especially if they are severe, abrupt in onset, or were not part of the patient's presenting symptoms. Symptoms such as these may be associated with an increased risk for suicidal thinking and behavior and indicate a need for very close monitoring and possibly changes in the medication.

Interference with Cognitive and Motor Performance

Clinical studies were performed to examine the effects of venlafaxine on behavioral performance of healthy individuals. The results revealed no clinically significant impairment of psychomotor, cognitive, or complex behavior performance. However, since any psychoactive drug may impair judgment, thinking, or motor skills, patients should be cautioned about operating hazardous machinery, including automobiles, until they are reasonably certain that venlafaxine therapy does not adversely affect their ability to engage in such activities.

Concomitant Medication

Patients should be advised to inform their physicians if they are taking, or plan to take, any prescription or over-the-counter drugs, including herbal preparations and nutritional supplements, since there is a potential for interactions.

Patients should be cautioned about the risk of serotonin syndrome with the concomitant use of venlafaxine hydrochloride extended-release capsules and triptans, tramadol, tryptophan supplements or other serotonergic agents (see CONTRAINDICATIONS and WARNINGS, Serotonin Syndrome and PRECAUTIONS, Drug Interactions, CNS-Active Drugs, Serotonergic Drugs).

Patients should be advised that taking venlafaxine hydrochloride can cause mild pupillary dilation, which in susceptible individuals, can lead to an episode of angle closure glaucoma. Pre-existing glaucoma is almost always open-angle glaucoma because angle closure glaucoma, when diagnosed, can be treated definitively with iridectomy. Open-angle glaucoma is not a risk factor for angle closure glaucoma. Patients may wish to be examined to determine whether they are susceptible to angle closure, and have a prophylactic procedure (e.g., iridectomy), if they are susceptible.

Patients should be cautioned about the concomitant use of venlafaxine hydrochloride extended-release capsules and NSAIDs, aspirin, warfarin, or other drugs that affect coagulation since combined use of psychotropic drugs that interfere with serotonin reuptake and these agents has been associated with an increased risk of bleeding (see PRECAUTIONS, Abnormal Bleeding).

Alcohol

Although venlafaxine has not been shown to increase the impairment of mental and motor skills caused by alcohol, patients should be advised to avoid alcohol while taking venlafaxine.

Allergic Reactions

Patients should be advised to notify their physician if they develop a rash, hives, or a related allergic phenomenon.

Pregnancy

Patients should be advised to notify their physician if they become pregnant or intend to become pregnant during therapy.

Nursing

Patients should be advised to notify their physician if they are breast-feeding an infant.

Laboratory Tests

There are no specific laboratory tests recommended.

Drug Interactions

As with all drugs, the potential for interaction by a variety of mechanisms is a possibility.

Alcohol

A single dose of ethanol (0.5 g/kg) had no effect on the pharmacokinetics of venlafaxine or O-desmethylvenlafaxine (ODV) when venlafaxine was administered at 150 mg/day in 15 healthy male subjects. Additionally, administration of venlafaxine in a stable regimen did not exaggerate the psychomotor and psychometric effects induced by ethanol in these same subjects when they were not receiving venlafaxine.

Cimetidine

Concomitant administration of cimetidine and venlafaxine in a steady-state study for both drugs resulted in inhibition of first-pass metabolism of venlafaxine in 18 healthy subjects. The oral clearance of venlafaxine was reduced by about 43%, and the exposure (AUC) and maximum concentration (Cmax) of the drug were increased by about 60%. However, coadministration of cimetidine had no apparent effect on the pharmacokinetics of ODV, which is present in much greater quantity in the circulation than venlafaxine. The overall pharmacological activity of venlafaxine plus ODV is expected to increase only slightly, and no dosage adjustment should be necessary for most normal adults. However, for patients with pre-existing hypertension, and for elderly patients or patients with hepatic dysfunction, the interaction associated with the concomitant use of venlafaxine and cimetidine is not known and potentially could be more pronounced. Therefore, caution is advised with such patients.

Diazepam

Under steady-state conditions for venlafaxine administered at 150 mg/day, a single 10 mg dose of diazepam did not appear to affect the pharmacokinetics of either venlafaxine or ODV in 18 healthy male subjects. Venlafaxine also did not have any effect on the pharmacokinetics of diazepam or its active metabolite, desmethyldiazepam, or affect the psychomotor and psychometric effects induced by diazepam.

Haloperidol

Venlafaxine administered under steady-state conditions at 150 mg/day in 24 healthy subjects decreased total oral-dose clearance (Cl/F) of a single 2 mg dose of haloperidol by 42%, which resulted in a 70% increase in haloperidol AUC. In addition, the haloperidol Cmax increased 88% when coadministered with venlafaxine, but the haloperidol elimination half-life (t1/2) was unchanged. The mechanism explaining this finding is unknown.

Lithium

The steady-state pharmacokinetics of venlafaxine administered at 150 mg/day were not affected when a single 600 mg oral dose of lithium was administered to 12 healthy male subjects. ODV also was unaffected. Venlafaxine had no effect on the pharmacokinetics of lithium (see also CNS-Active Drugs, below).

Drugs Highly Bound to Plasma Proteins

Venlafaxine is not highly bound to plasma proteins; therefore, administration of venlafaxine hydrochloride extended-release capsules to a patient taking another drug that is highly protein bound should not cause increased free concentrations of the other drug.

Drugs that Interfere with Hemostasis (e.g., NSAIDs, Aspirin, and Warfarin)

Serotonin release by platelets plays an important role in hemostasis. Epidemiological studies of the case-control and cohort design that have demonstrated an association between use of psychotropic drugs that interfere with serotonin reuptake and the occurrence of upper gastrointestinal bleeding have also shown that concurrent use of an NSAID or aspirin may potentiate this risk of bleeding. Altered anticoagulant effects, including increased bleeding, have been reported when SSRIs and SNRIs are coadministered with warfarin. Patients receiving warfarin therapy should be carefully monitored when venlafaxine hydrochloride extended-release capsules are initiated or discontinued.

Drugs that Inhibit Cytochrome P450 Isoenzymes

CYP2D6 Inhibitors: In vitro and in vivo studies indicate that venlafaxine is metabolized to its active metabolite, ODV, by CYP2D6, the isoenzyme that is responsible for the genetic polymorphism seen in the metabolism of many antidepressants. Therefore, the potential exists for a drug interaction between drugs that inhibit CYP2D6-mediated metabolism of venlafaxine, reducing the metabolism of venlafaxine to ODV, resulting in increased plasma concentrations of venlafaxine and decreased concentrations of the active metabolite. CYP2D6 inhibitors such as quinidine would be expected to do this, but the effect would be similar to what is seen in patients who are genetically CYP2D6 poor metabolizers (see Metabolism and Excretion under CLINICAL PHARMACOLOGY). Therefore, no dosage adjustment is required when venlafaxine is coadministered with a CYP2D6 inhibitor.

Ketoconazole: A pharmacokinetic study with ketoconazole 100 mg b.i.d. with a single dose of venlafaxine 50 mg in extensive metabolizers (EM; n = 14) and 25 mg in poor metabolizers (PM; n = 6) of CYP2D6 resulted in higher plasma concentrations of both venlafaxine and O-desmethylvenlafaxine (ODV) in most subjects following administration of ketoconazole. Venlafaxine Cmax increased by 26% in EM subjects and 48% in PM subjects. Cmax values for ODV increased by 14% and 29% in EM and PM subjects, respectively.

Venlafaxine AUC increased by 21% in EM subjects and 70% in PM subjects (range in PMs -2% to 206%), and AUC values for ODV increased by 23% and 33% in EM and PM (range in PMs -38% to 105%) subjects, respectively. Combined AUCs of venlafaxine and ODV increased on average by approximately 23% in EMs and 53% in PMs (range in PMs 4% to 134%).

Concomitant use of CYP3A4 inhibitors and venlafaxine may increase levels of venlafaxine and ODV. Therefore, caution is advised if a patient's therapy includes a CYP3A4 inhibitor and venlafaxine concomitantly.

Drugs Metabolized by Cytochrome P450 Isoenzymes

CYP2D6: In vitro studies indicate that venlafaxine is a relatively weak inhibitor of CYP2D6. These findings have been confirmed in a clinical drug interaction study comparing the effect of venlafaxine with that of fluoxetine on the CYP2D6-mediated metabolism of dextromethorphan to dextrorphan.

Imipramine - Venlafaxine did not affect the pharmacokinetics of imipramine and 2-OH-imipramine. However, desipramine AUC, Cmax, and Cmin increased by about 35% in the presence of venlafaxine. The 2-OH-desipramine AUC's increased by at least 2.5 fold (with venlafaxine 37.5 mg q12h) and by 4.5 fold (with venlafaxine 75 mg q12h). Imipramine did not affect the pharmacokinetics of venlafaxine and ODV. The clinical significance of elevated 2-OH-desipramine levels is unknown.

Metoprolol - Concomitant administration of venlafaxine (50 mg every 8 hours for 5 days) and metoprolol (100 mg every 24 hours for 5 days) to 18 healthy male subjects in a pharmacokinetic interaction study for both drugs resulted in an increase of plasma concentrations of metoprolol by approximately 30-40% without altering the plasma concentrations of its active metabolite, α-hydroxymetoprolol. Metoprolol did not alter the pharmacokinetic profile of venlafaxine or its active metabolite, O-desmethylvenlafaxine.

Venlafaxine appeared to reduce the blood pressure lowering effect of metoprolol in this study. The clinical relevance of this finding for hypertensive patients is unknown. Caution should be exercised with co-administration of venlafaxine and metoprolol.

Venlafaxine treatment has been associated with dose-related increases in blood pressure in some patients. It is recommended that patients receiving venlafaxine hydrochloride extended-release capsules have regular monitoring of blood pressure (see WARNINGS).

Risperidone - Venlafaxine administered under steady-state conditions at 150 mg/day slightly inhibited the CYP2D6-mediated metabolism of risperidone (administered as a single 1 mg oral dose) to its active metabolite, 9-hydroxyrisperidone, resulting in an approximate 32% increase in risperidone AUC. However, venlafaxine coadministration did not significantly alter the pharmacokinetic profile of the total active moiety (risperidone plus 9-hydroxyrisperidone).

CYP3A4: Venlafaxine did not inhibit CYP3A4 in vitro. This finding was confirmed in vivo by clinical drug interaction studies in which venlafaxine did not inhibit the metabolism of several CYP3A4 substrates, including alprazolam, diazepam, and terfenadine.

Indinavir - In a study of 9 healthy volunteers, venlafaxine administered under steady-state conditions at 150 mg/day resulted in a 28% decrease in the AUC of a single 800 mg oral dose of indinavir and a 36% decrease in indinavir Cmax. Indinavir did not affect the pharmacokinetics of venlafaxine and ODV. The clinical significance of this finding is unknown.

CYP1A2: Venlafaxine did not inhibit CYP1A2 in vitro. This finding was confirmed in vivo by a clinical drug interaction study in which venlafaxine did not inhibit the metabolism of caffeine, a CYP1A2 substrate.

CYP2C9: Venlafaxine did not inhibit CYP2C9 in vitro. In vivo, venlafaxine 75 mg by mouth every 12 hours did not alter the pharmacokinetics of a single 500 mg dose of tolbutamide or the CYP2C9 mediated formation of 4-hydroxy-tolbutamide.

CYP2C19: Venlafaxine did not inhibit the metabolism of diazepam, which is partially metabolized by CYP2C19 (see Diazepam above).

Monoamine Oxidase Inhibitors

See CONTRAINDICATIONS, WARNINGS, and DOSAGE AND ADMINISTRATION.

CNS-Active Drugs

The risk of using venlafaxine in combination with other CNS-active drugs has not been systematically evaluated (except in the case of those CNS-active drugs noted above). Consequently, caution is advised if the concomitant administration of venlafaxine and such drugs is required. (See CONTRAINDICATIONS and WARNINGS)

Serotonergic Drugs: see CONTRAINDICATIONS, WARNINGS, and DOSAGE AND ADMINISTRATION.

Triptans: There have been rare postmarketing reports of serotonin syndrome with use of an SSRI and a triptan. If concomitant treatment of venlafaxine hydrochloride extended-release capsules with a triptan is clinically warranted, careful observation of the patient is advised, particularly during treatment initiation and dose increases (see WARNINGS, Serotonin Syndrome).

Drug-Laboratory Test Interactions

False-positive urine immunoassay screening tests for phencyclidine (PCP) and amphetamine have been reported in patients taking venlafaxine. This is due to lack of specificity of the screening tests. False positive test results may be expected for several days following discontinuation of venlafaxine therapy. Confirmatory tests, such as gas chromatography/mass spectrometry, will distinguish venlafaxine from PCP and amphetamine.

Electroconvulsive Therapy

There are no clinical data establishing the benefit of electroconvulsive therapy combined with venlafaxine hydrochloride extended-release capsule treatment.

Postmarketing Spontaneous Drug Interaction Reports

See ADVERSE REACTIONS, Postmarketing Reports.

Carcinogenesis, Mutagenesis, Impairment of FertilityCarcinogenesis

Venlafaxine was given by oral gavage to mice for 18 months at doses up to 120 mg/kg per day, which was 1.7 times the maximum recommended human dose on a mg/m2 basis. Venlafaxine was also given to rats by oral gavage for 24 months at doses up to 120 mg/kg per day. In rats receiving the 120 mg/kg dose, plasma concentrations of venlafaxine at necropsy were 1 times (male rats) and 6 times (female rats) the plasma concentrations of patients receiving the maximum recommended human dose. Plasma levels of the O-desmethyl metabolite were lower in rats than in patients receiving the maximum recommended dose. Tumors were not increased by venlafaxine treatment in mice or rats.

Mutagenesis

Venlafaxine and the major human metabolite, O-desmethylvenlafaxine (ODV), were not mutagenic in the Ames reverse mutation assay in Salmonella bacteria or the Chinese hamster ovary/HGPRT mammalian cell forward gene mutation assay. Venlafaxine was also not mutagenic or clastogenic in the in vitro BALB/c-3T3 mouse cell transformation assay, the sister chromatid exchange assay in cultured Chinese hamster ovary cells, or in the in vivo chromosomal aberration assay in rat bone marrow. ODV was not clastogenic in the in vitro Chinese hamster ovary cell chromosomal aberration assay, but elicited a clastogenic response in the in vivo chromosomal aberration assay in rat bone marrow.

Impairment of Fertility

Reproduction and fertility studies in rats showed no effects on male or female fertility at oral doses of up to 2 times the maximum recommended human dose on a mg/m2 basis.

PregnancyTeratogenic Effects - Pregnancy Category C

Venlafaxine did not cause malformations in offspring of rats or rabbits given doses up to 2.5 times (rat) or 4 times (rabbit) the maximum recommended human daily dose on a mg/m2 basis. However, in rats, there was a decrease in pup weight, an increase in stillborn pups, and an increase in pup deaths during the first 5 days of lactation, when dosing began during pregnancy and continued until weaning. The cause of these deaths is not known. These effects occurred at 2.5 times (mg/m2) the maximum human daily dose. The no effect dose for rat pup mortality was 0.25 times the human dose on a mg/m2 basis. There are no adequate and well-controlled studies in pregnant women. Because animal reproduction studies are not always predictive of human response, this drug should be used during pregnancy only if clearly needed.

Non-teratogenic Effects

Neonates exposed to venlafaxine hydrochloride extended-release capsules, other SNRIs (Serotonin and Norepinephrine Reuptake Inhibitors), or SSRIs (Selective Serotonin Reuptake Inhibitors), late in the third trimester have developed complications requiring prolonged hospitalization, respiratory support, and tube feeding. Such complications can arise immediately upon delivery. Reported clinical findings have included respiratory distress, cyanosis, apnea, seizures, temperature instability, feeding difficulty, vomiting, hypoglycemia, hypotonia, hypertonia, hyperreflexia, tremor, jitteriness, irritability, and constant crying. These features are consistent with either a direct toxic effect of SSRIs and SNRIs or, possibly, a drug discontinuation syndrome. It should be noted that, in some cases, the clinical picture is consistent with serotonin syndrome (see PRECAUTIONS-Drug Interactions-CNS-Active Drugs). When treating a pregnant woman with venlafaxine hydrochloride extended-release capsules during the third trimester, the physician should carefully consider the potential risks and benefits of treatment (see DOSAGE AND ADMINISTRATION).

Labor and Delivery

The effect of venlafaxine on labor and delivery in humans is unknown.

Nursing Mothers

Venlafaxine and ODV have been reported to be excreted in human milk. Because of the potential for serious adverse reactions in nursing infants from venlafaxine hydrochloride extended-release capsules, a decision should be made whether to discontinue nursing or to discontinue the drug, taking into account the importance of the drug to the mother.

Pediatric Use

Safety and effectiveness in the pediatric population have not been established (see BOX WARNING and WARNINGS, Clinical Worsening and Suicide Risk). Two placebo-controlled trials in 766 pediatric patients with MDD and two placebo-controlled trials in 793 pediatric patients with GAD have been conducted with venlafaxine hydrochloride extended-release capsules, and the data were not sufficient to support a claim for use in pediatric patients.

Anyone considering the use of venlafaxine hydrochloride extended-release capsules in a child or adolescent must balance the potential risks with the clinical need.

Although no studies have been designed to primarily assess venlafaxine hydrochloride extended-release capsules' impact on the growth, development, and maturation of children and adolescents, the studies that have been done suggest that venlafaxine hydrochloride extended-release capsules may adversely affect weight and height (see PRECAUTIONS, General, Changes in Height and Changes in Weight). Should the decision be made to treat a pediatric patient with venlafaxine hydrochloride extended-release capsules, regular monitoring of weight and height is recommended during treatment, particularly if it is to be continued long term. The safety of venlafaxine hydrochloride extended-release capsules treatment for pediatric patients has not been systematically assessed for chronic treatment longer than six months in duration.

In the studies conducted in pediatric patients (ages 6-17), the occurrence of blood pressure and cholesterol increases considered to be clinically relevant in pediatric patients was similar to that observed in adult patients. Consequently, the precautions for adults apply to pediatric patients (see WARNINGS, Sustained Hypertension, and PRECAUTIONS, General, Serum Cholesterol Elevation).

Geriatric Use

Approximately 4% (14/357), 6% (77/1381), 1% (10/819), and 2% (16/1001) of venlafaxine hydrochloride extended-release capsule-treated patients in placebo-controlled premarketing major depressive disorder, GAD, Social Anxiety Disorder trials, and panic disorder trials, respectively, were 65 years of age or over. Of 2,897 venlafaxine hydrochloride tablet-treated (immediate release) patients in premarketing phase major depressive disorder studies, 12% (357) were 65 years of age or over. No overall differences in effectiveness or safety were observed between geriatric patients and younger patients, and other reported clinical experience generally has not identified differences in response between the elderly and younger patients. However, greater sensitivity of some older individuals cannot be ruled out. SSRIs and SNRIs, including venlafaxine hydrochloride extended-release capsules have been associated with cases of clinically significant hyponatremia in elderly patients, who may be at greater risk for this adverse event (see PRECAUTIONS, Hyponatremia).

The pharmacokinetics of venlafaxine and ODV are not substantially altered in the elderly (see CLINICAL PHARMACOLOGY). No dose adjustment is recommended for the elderly on the basis of age alone, although other clinical circumstances, some of which may be more common in the elderly, such as renal or hepatic impairment, may warrant a dose reduction (see DOSAGE AND ADMINISTRATION).

ADVERSE REACTIONS SECTION

The information included in the Adverse Findings Observed in Short-Term, Placebo-Controlled Studies with Venlafaxine Hydrochloride Extended-Release Capsules subsection is based on data from a pool of three 8- and 12-week controlled clinical trials in major depressive disorder (includes two U.S. trials and one European trial), on data up to 8 weeks from a pool of five controlled clinical trials in GAD with venlafaxine hydrochloride extended-release capsules , on data up to 12 weeks from a pool of five controlled clinical trials in Social Anxiety Disorder, and on data up to 12 weeks from a pool of four controlled clinical trials in panic disorder. Information on additional adverse events associated with venlafaxine hydrochloride extended-release capsules in the entire development program for the formulation and with venlafaxine hydrochloride tablets(immediate release) is included in the Other Adverse Events Observed During the Premarketing Evaluation of Venlafaxine Hydrochloride Tablets and Venlafaxine Hydrochloride Extended-Release Capsules subsection (see also WARNINGS and PRECAUTIONS).

Adverse Findings Observed in Short-Term, Placebo-Controlled Studies with Venlafaxine Hydrochloride Extended-Release CapsulesAdverse Events Associated with Discontinuation of Treatment

Approximately 11% of the 357 patients who received venlafaxine hydrochloride extended-release capsules in placebo-controlled clinical trials for major depressive disorder discontinued treatment due to an adverse experience, compared with 6% of the 285 placebo-treated patients in those studies. Approximately 18% of the 1381 patients who received venlafaxine hydrochloride extended-release capsules in placebo-controlled clinical trials for GAD discontinued treatment due to an adverse experience, compared with 12% of the 555 placebo-treated patients in those studies. Approximately 15% of the 819 patients who received venlafaxine hydrochloride extended-release capsules in placebo-controlled clinical trials for Social Anxiety Disorder discontinued treatment due to an adverse experience, compared with 5% of the 695 placebo-treated patients in those studies. Approximately 7% of the 1,001 patients who received venlafaxine hydrochloride extended-release capsules in placebo-controlled clinical trials for panic disorder discontinued treatment due to an adverse experience, compared with 6% of the 662 placebo-treated patients in those studies. The most common events leading to discontinuation and considered to be drug-related (ie, leading to discontinuation in at least 1% of the venlafaxine hydrochloride extended-release capsule-treated patients at a rate at least twice that of placebo for any indication) are shown in Table 6.

Table 6 Common Adverse Events Leading to Discontinuation of Treatment in Placebo-Controlled Trials *
 | Percentage of Patients Discontinuing Due to Adverse Event
Adverse Event | Major Depressive Disorder Indication † | GAD Indication ‡, § | Social Anxiety Disorder Indication ¶ | Panic Disorder Indication
 | Venlafaxine hydrochloride extended-release capsules n = 357 | Placebo n = 285 | Venlafaxine hydrochloride extended-release capsules n = 1381 | Placebo n = 555 | Venlafaxine hydrochloride extended-release capsules n = 819 | Placebo n = 695 | Venlafaxine hydrochloride extended-release capsules n = 1001 | Placebo n = 662
Body as a Whole
Asthenia | -- | -- | 3% | <1% | 2% | <1% | 1% | 0%
Headache | -- | -- | -- | -- | 1% | <1% | -- | --
Digestive System
Nausea | 4% | <1% | 8% | <1% | 3% | <1% | 2% | <1%
Anorexia | 1% | <1% | -- | -- | -- | -- | -- | --
Dry Mouth | 1% | 0% | 2% | <1% | -- | -- | -- | --
Vomiting | -- | -- | 1% | <1% | -- | -- | -- | --
Nervous System
Dizziness | 2% | 1% | -- | -- | 2% | <1% | -- | --
Insomnia | 1% | <1% | 3% | <1% | 2% | <1% | 1% | 1%
Somnolence | 2% | <1% | 3% | <1% | 2% | <1% | -- | --
Nervousness | -- | -- | 2% | <1% | -- | -- | -- | --
Tremor | -- | -- | 1% | 0% | -- | -- | -- | --
Skin
Sweating | -- | -- | 2% | <1% | -- | -- | -- | --
Urogenital System
Impotence # | -- | -- | -- | -- | 2% | 0% | -- | --
*Two of the major depressive disorder studies were flexible dose and one was fixed dose. Four of the GAD studies were fixed dose and one was flexible dose. Four of the Social Anxiety Disorder studies were flexible dose and one was fixed/flexible dose. Two of the panic disorder studies were flexible dose and two were fixed dose. †In U.S. placebo-controlled trials for major depressive disorder, the following were also common events leading to discontinuation and were considered to be drug-related for venlafaxine hydrochloride extended-release capsule-treated patients (% venlafaxine hydrochloride extended-release capsules [n = 192], % Placebo [n = 202]): hypertension (1%, <1%); diarrhea (1%, 0%); paresthesia (1%, 0%); tremor (1%, 0%); abnormal vision, mostly blurred vision (1%, 0%); and abnormal, mostly delayed, ejaculation (1%, 0%). ‡In two short-term U.S. placebo-controlled trials for GAD, the following were also common events leading to discontinuation and were considered to be drug-related for venlafaxine hydrochloride extended-release capsule-treated patients (% venlafaxine hydrochloride extended-release capsules [n = 476]), % Placebo [n = 201]: headache (4%, <1%); vasodilatation (1%, 0%); anorexia (2%, <1%); dizziness (4%, 1%); thinking abnormal (1%, 0%); and abnormal vision (1%, 0%). §In long-term placebo-controlled trials for GAD, the following was also a common event leading to discontinuation and was considered to be drug-related for venlafaxine hydrochloride extended-release capsule-treated patients (% venlafaxine hydrochloride extended-release capsules [n = 535], % Placebo [n = 257]): decreased libido (1%, 0%). ¶In a 6-month placebo-controlled trial for Social Anxiety Disorder, the following was also a common event leading to discontinuation and was considered to be drug-related for venlafaxine hydrochloride extended-release capsule-treated patients (% Venlafaxine hydrochloride extended-release capsules [n = 257], % Placebo [n = 129]: depression (5%, 0%), libido decrease (1%, 0%), and nervousness (3%, 0%). #Incidence is based on the number of men (venlafaxine hydrochloride extended-release capsules = 454, placebo = 357).

Adverse Events Occurring at an Incidence of 2% or More Among Venlafaxine Hydrochloride Extended-Release Capsule-Treated Patients

Tables 7, 8, 9, and 10 enumerate the incidence, rounded to the nearest percent, of treatment-emergent adverse events that occurred during acute therapy of major depressive disorder (up to 12 weeks; dose range of 75 to 225 mg/day), of GAD (up to 8 weeks; dose range of 37.5 to 225 mg/day), of Social Anxiety Disorder (up to 12 weeks; dose range of 75 to 225 mg/day), and of panic disorder (up to 12 weeks; dose range of 37.5 to 225 mg/day), respectively, in 2% or more of patients treated with venlafaxine hydrochloride extended-release capsules where the incidence in patients treated with venlafaxine hydrochloride extended-release capsules was greater than the incidence for the respective placebo-treated patients. The table shows the percentage of patients in each group who had at least one episode of an event at some time during their treatment. Reported adverse events were classified using a standard COSTART-based Dictionary terminology.

The prescriber should be aware that these figures cannot be used to predict the incidence of side effects in the course of usual medical practice where patient characteristics and other factors differ from those which prevailed in the clinical trials. Similarly, the cited frequencies cannot be compared with figures obtained from other clinical investigations involving different treatments, uses and investigators. The cited figures, however, do provide the prescribing physician with some basis for estimating the relative contribution of drug and nondrug factors to the side effect incidence rate in the population studied.

Commonly Observed Adverse Events from Tables 7, 8, 9, and 10:

Major Depressive Disorder

Note in particular the following adverse events that occurred in at least 5% of the venlafaxine hydrochloride extended-release capsule patients and at a rate at least twice that of the placebo group for all placebo-controlled trials for the major depressive disorder indication (Table 7): Abnormal ejaculation, gastrointestinal complaints (nausea, dry mouth, and anorexia), CNS complaints (dizziness, somnolence, and abnormal dreams), and sweating. In the two U.S. placebo-controlled trials, the following additional events occurred in at least 5% of venlafaxine hydrochloride extended-release capsule-treated patients (n = 192) and at a rate at least twice that of the placebo group: Abnormalities of sexual function (impotence in men, anorgasmia in women, and libido decreased), gastrointestinal complaints (constipation and flatulence), CNS complaints (insomnia, nervousness, and tremor), problems of special senses (abnormal vision), cardiovascular effects (hypertension and vasodilatation), and yawning.

Generalized Anxiety Disorder

Note in particular the following adverse events that occurred in at least 5% of the venlafaxine hydrochloride extended-release capsule patients and at a rate at least twice that of the placebo group for all placebo-controlled trials for the GAD indication (Table 8): Abnormalities of sexual function (abnormal ejaculation and impotence), gastrointestinal complaints (nausea, dry mouth, anorexia, and constipation), problems of special senses (abnormal vision), and sweating.

Social Anxiety Disorder

Note in particular the following adverse events that occurred in at least 5% of the venlafaxine hydrochloride extended-release capsule patients and at a rate at least twice that of the placebo group for the 5 placebo-controlled trials for the Social Anxiety Disorder indication (Table 9): Asthenia, gastrointestinal complaints (anorexia, constipation, dry mouth, nausea), CNS complaints (insomnia, libido decreased, nervousness, somnolence, tremor), abnormalities of sexual function (abnormal ejaculation, impotence), yawn, and sweating.

In the 6-month trial, the following adverse events occurred twice as often in the 150-225 mg/day venlafaxine hydrochloride extended-release capsule group compared to the 75 mg/day venlafaxine hydrochloride extended-release capsule group and placebo: vasodilation, libido decreased, tremor, yawn, abnormal vision, and impotence.

Panic Disorder

Note in particular the following adverse events that occurred in at least 5% of the venlafaxine hydrochloride extended-release capsule patients and at a rate at least twice that of the placebo group for 4 placebo-controlled trials for the panic disorder indication (Table 10): gastrointestinal complaints (anorexia, constipation, dry mouth), CNS complaints (somnolence, tremor), abnormalities of sexual function (abnormal ejaculation), and sweating.

Table 7 Treatment-Emergent Adverse Event Incidence in Short-Term Placebo-Controlled Venlafaxine Hydrochloride Extended-Release Capsule Clinical Trials in Patients with Major Depressive Disorder *, †
 | % Reporting Event
Body System Preferred Term | Venlafaxine hydrochloride extended-release capsules (n = 357) | Placebo (n = 285)
Body as a Whole
Asthenia | 8% | 7%
Cardiovascular System
Vasodilatation ‡ | 4% | 2%
Hypertension | 4% | 1%
Digestive System
Nausea | 31% | 12%
Constipation | 8% | 5%
Anorexia | 8% | 4%
Vomiting | 4% | 2%
Flatulence | 4% | 3%
Metabolic/Nutritional
Weight Loss | 3% | 0%
Nervous System
Dizziness | 20% | 9%
Somnolence | 17% | 8%
Insomnia | 17% | 11%
Dry Mouth | 12% | 6%
Nervousness | 10% | 5%
Abnormal Dreams § | 7% | 2%
Tremor | 5% | 2%
Depression | 3% | <1%
Paresthesia | 3% | 1%
Libido Decreased | 3% | <1%
Agitation | 3% | 1%
Respiratory System
Pharyngitis | 7% | 6%
Yawn | 3% | 0%
Skin
Sweating | 14% | 3%
Special Senses
Abnormal Vision ¶ | 4% | <1%
Urogenital System
Abnormal Ejaculation | 16% | <1%
(male) #, Þ
Impotence Þ | 4% | <1%
Anorgasmia (female) ß, à | 3% | <1%
*Incidence, rounded to the nearest %, for events reported by at least 2% of patients treated with venlafaxine hydrochloride extended-release capsules, except the following events which had an incidence equal to or less than placebo: abdominal pain, accidental injury, anxiety, back pain, bronchitis, diarrhea, dysmenorrhea, dyspepsia, flu syndrome, headache, infection, pain, palpitation, rhinitis, and sinusitis. †<1% indicates an incidence greater than zero but less than 1%. ‡Mostly "hot flashes." §Mostly "vivid dreams," "nightmares," and "increased dreaming." ¶Mostly "blurred vision" and "difficulty focusing eyes." #Mostly "delayed ejaculation." ÞIncidence is based on the number of male patients. ßMostly "delayed orgasm" or "anorgasmia." àIncidence is based on the number of female patients.

Table 8 Treatment-Emergent Adverse Event Incidence in Short-Term Placebo-Controlled Venlafaxine Hydrochloride Extended-Release Capsule Clinical Trials in GAD Patients *, †
 | % Reporting Event
Body System Preferred Term | Venlafaxine hydrochloride extended-release capsules (n = 1381) | Placebo (n = 555)
Body as a Whole
Asthenia | 12% | 8%
Cardiovascular System
Vasodilatation ‡ | 4% | 2%
Digestive System
Nausea | 35% | 12%
Constipation | 10% | 4%
Anorexia | 8% | 2%
Vomiting | 5% | 3%
Nervous System
Dizziness | 16% | 11%
Dry Mouth | 16% | 6%
Insomnia | 15% | 10%
Somnolence | 14% | 8%
Nervousness | 6% | 4%
Libido Decreased | 4% | 2%
Tremor | 4% | <1%
Abnormal Dreams § | 3% | 2%
Hypertonia | 3% | 2%
Paresthesia | 2% | 1%
Respiratory System
Yawn | 3% | <1%
Skin
Sweating | 10% | 3%
Special Senses
Abnormal Vision ¶ | 5% | <1%
Urogenital System
Abnormal Ejaculation #, Þ | 11% | <1%
Impotence Þ | 5% | <1%
Orgasmic Dysfunction (female) ß, à | 2% | 0%
*Adverse events for which the venlafaxine hydrochloride extended-release capsules reporting rate was less than or equal to the placebo rate are not included. These events are: abdominal pain, accidental injury, anxiety, back pain, diarrhea, dysmenorrhea, dyspepsia, flu syndrome, headache, infection, myalgia, pain, palpitation, pharyngitis, rhinitis, tinnitus, and urinary frequency. †<1% means greater than zero but less than 1%. ‡Mostly "hot flashes." §Mostly "vivid dreams," "nightmares," and "increased dreaming." ¶Mostly "blurred vision" and "difficulty focusing eyes." #Includes "delayed ejaculation" and "anorgasmia." ÞPercentage based on the number of males (venlafaxine hydrochloride extended-release capsules = 525, placebo = 220). ßIncludes "delayed orgasm," "abnormal orgasm," and "anorgasmia." àPercentage based on the number of females (venlafaxine hydrochloride extended-release capsules = 856, placebo = 335).

Table 9 Treatment-Emergent Adverse Event Incidence in Short-Term Placebo-Controlled Venlafaxine Hydrochloride Extended-Release Capsule Clinical Trials in Social Anxiety Disorder Patients *, †
 | % Reporting Event
Body System Preferred Term | Venlafaxine hydrochloride extended-release capsules (n = 819) | Placebo (n = 695)
Body as a Whole
Headache | 38% | 34%
Asthenia | 19% | 9%
Abdominal Pain | 6% | 4%
Accidental Injury | 4% | 3%
Cardiovascular System
Hypertension | 5% | 3%
Vasodilatation ‡ | 3% | 2%
Palpitation | 3% | 1%
Digestive System
Nausea | 31% | 9%
Anorexia § | 17% | 2%
Constipation | 9% | 3%
Diarrhea | 8% | 6%
Dyspepsia | 7% | 6%
Vomiting | 3% | 2%
Metabolic/Nutritional
Weight Loss | 2% | <1%
Nervous System
Insomnia | 24% | 8%
Somnolence | 20% | 8%
Dry Mouth | 17% | 4%
Dizziness | 16% | 8%
Nervousness | 10% | 5%
Libido Decreased | 8% | 2%
Anxiety | 5% | 4%
Tremor | 5% | 2%
Agitation | 3% | 1%
Abnormal Dreams ¶ | 3% | <1%
Twitching | 3% | <1%
Respiratory System
Yawn | 5% | <1%
Skin
Sweating | 13% | 4%
Special Senses
Abnormal Vision # | 4% | 2%
Urogenital System
Abnormal Ejaculation Þ, ß | 19% | <1%
Impotence ß | 6% | <1%
Orgasmic Dysfunction à, è | 5% | <1%
*Adverse events for which the venlafaxine hydrochloride extended-release capsules reporting rate was less than or equal to the placebo rate are not included. These events are: arthralgia, back pain, dysmenorrhea, flu syndrome, infection, pain, pharyngitis, rhinitis, and upper respiratory infection. †<1% means greater than zero but less than 1%. ‡Mostly "hot flashes." §Mostly "decreased appetite" and "loss of appetite." ¶Mostly "vivid dreams," "nightmares," and "increased dreaming." #Mostly "blurred vision." ÞIncludes "delayed ejaculation" and "anorgasmia." ßPercentage based on the number of males (venlafaxine hydrochloride extended-release capsules = 454, placebo = 357). àIncludes "abnormal orgasm" and "anorgasmia." èPercentage based on the number of females (venlafaxine hydrochloride extended-release capsules = 365, placebo = 338).

Table 10 Treatment-Emergent Adverse Event Incidence in Short-Term Placebo-Controlled Venlafaxine Hydrochloride Extended-Release Capsule Clinical Trials in Panic Disorder Patients *, †
 | % Reporting Event
Body System Preferred Term | Venlafaxine hydrochloride extended-release capsule (n = 1001) | Placebo (n = 662)
Body as a Whole
Asthenia | 10% | 8%
Cardiovascular System
Hypertension | 4% | 3%
Vasodilatation ‡ | 3% | 2%
Digestive System
Nausea | 21% | 14%
Dry mouth | 12% | 6%
Constipation | 9% | 3%
Anorexia § | 8% | 3%
Nervous System
Insomnia | 17% | 9%
Somnolence | 12% | 6%
Dizziness | 11% | 10%
Tremor | 5% | 2%
Libido Decreased | 4% | 2%
Skin
Sweating | 10% | 2%
Urogenital System
Abnormal Ejaculation ¶, # | 8% | <1%
Impotence # | 4% | <1%
Orgasmic Dysfunction Þ, ß | 2% | <1%
*Adverse events for which the venlafaxine hydrochloride extended-release capsules reporting rate was less than or equal to the placebo rate are not included. These events are: abdominal pain, abnormal vision, accidental injury, anxiety, back pain, diarrhea, dysmenorrhea, dyspepsia, flu syndrome, headache, infection, nervousness, pain, paresthesia, pharyngitis, rash, rhinitis, and vomiting. †<1% means greater than zero but less than 1%. ‡Mostly "hot flushes." §Mostly "decreased appetite" and "loss of appetite." ¶Includes "delayed or retarded ejaculation" and "anorgasmia." #Percentage based on the number of males (venlafaxine hydrochloride extended-release capsule = 335, placebo = 238). ÞIncludes "anorgasmia" and "delayed orgasm." ßPercentage based on the number of females (venlafaxine hydrochloride extended-release capsules = 666, placebo = 424).

Vital Sign Changes

Venlafaxine hydrochloride extended-release capsules treatment for up to 12 weeks in premarketing placebo-controlled major depressive disorder trials was associated with a mean final on-therapy increase in pulse rate of approximately 2 beats per minute, compared with 1 beat per minute for placebo. Venlafaxine hydrochloride extended-release capsules treatment for up to 8 weeks in premarketing placebo-controlled GAD trials was associated with a mean final on-therapy increase in pulse rate of approximately 2 beats per minute, compared with less than 1 beat per minute for placebo. Venlafaxine hydrochloride extended-release capsules treatment for up to 12 weeks in premarketing placebo-controlled Social Anxiety Disorder trials was associated with a mean final on-therapy increase in pulse rate of approximately 3 beats per minute, compared with an increase of 1 beat per minute for placebo. Venlafaxine hydrochloride extended-release capsules treatment for up to 12 weeks in premarketing placebo-controlled panic disorder trials was associated with a mean final on-therapy increase in pulse rate of approximately 1 beat per minute, compared with a decrease of less than 1 beat per minute for placebo. (See the Sustained Hypertension and Elevations in Systolic and Diastolic Blood Pressure sections of WARNINGS for effects on blood pressure.)

In a flexible-dose study, with venlafaxine hydrochloride tablet (immediate release) doses in the range of 200 to 375 mg/day and mean dose greater than 300 mg/day, the mean pulse was increased by about 2 beats per minute compared with a decrease of about 1 beat per minute for placebo.

Laboratory ChangesSerum Cholesterol

Venlafaxine hydrochloride extended-release capsule treatment for up to 12 weeks in premarketing placebo-controlled trials for major depressive disorder was associated with a mean final on-therapy increase in serum cholesterol concentration of approximately 1.5 mg/dL compared with a mean final decrease of 7.4 mg/dL for placebo. Venlafaxine hydrochloride extended-release capsule treatment for up to 8 weeks and up to 6 months in premarketing placebo-controlled GAD trials was associated with mean final on-therapy increases in serum cholesterol concentration of approximately 1.0 mg/dL and 2.3 mg/dL, respectively while placebo subjects experienced mean final decreases of 4.9 mg/dL and 7.7 mg/dL, respectively. Venlafaxine hydrochloride extended-release capsule treatment for up to 12 weeks and up to 6 months in premarketing placebo-controlled Social Anxiety Disorder trials was associated with mean final on-therapy increases in serum cholesterol concentration of approximately 7.9 mg/dL and 5.6 mg/dL, respectively, compared with mean final decreases of 2.9 and 4.2 mg/dL, respectively, for placebo. Venlafaxine hydrochloride extended-release capsule treatment for up to 12 weeks in premarketing placebo-controlled panic disorder trials was associated with mean final on-therapy increases in serum cholesterol concentration of approximately 5.8 mg/dL compared with a mean final decrease of 3.7 mg/dL for placebo.

Patients treated with venlafaxine hydrochloride tablets (immediate release) for at least 3 months in placebo-controlled 12-month extension trials had a mean final on-therapy increase in total cholesterol of 9.1 mg/dL compared with a decrease of 7.1 mg/dL among placebo-treated patients. This increase was duration dependent over the study period and tended to be greater with higher doses. Clinically relevant increases in serum cholesterol, defined as 1) a final on-therapy increase in serum cholesterol ≥50 mg/dL from baseline and to a value ≥261 mg/dL, or 2) an average on-therapy increase in serum cholesterol ≥50 mg/dL from baseline and to a value ≥261 mg/dL, were recorded in 5.3% of venlafaxine-treated patients and 0.0% of placebo-treated patients (see PRECAUTIONS-General-Serum Cholesterol Elevation).

Serum Triglycerides

Venlafaxine hydrochloride extended-release capsule treatment for up to 12 weeks in pooled premarketing Social Anxiety Disorder trials was associated with a mean final on-therapy increase in fasting serum triglyceride concentration of approximately 8.2 mg/dL, compared with a mean final increase of 0.4 mg/dL for placebo. Venlafaxine hydrochloride extended-release capsule treatment for up to 6 months in a premarketing Social Anxiety Disorder trial was associated with a mean final on-therapy increase in fasting serum triglyceride concentration of approximately 11.8 mg/dL, compared with a mean final on-therapy increase of 1.8 mg/dL for placebo.

Venlafaxine hydrochloride extended-release capsule treatment for up to 12 weeks in pooled premarketing Panic Disorder trials was associated with a mean final on-therapy increase in fasting serum triglyceride concentration of approximately 5.9 mg/dL, compared with a mean final increase of 0.9 mg/dL for placebo. Venlafaxine hydrochloride extended-release capsule treatment for up to 6 months in a premarketing Panic Disorder trial was associated with a mean final on-therapy increase in fasting serum triglyceride concentration of approximately 9.3 mg/dL, compared with a mean final on-therapy decrease of 0.3 mg/dL for placebo.

ECG Changes

In a flexible-dose study, with venlafaxine hydrochloride tablet (immediate release) doses in the range of 200 to 375 mg/day and mean dose greater than 300 mg/day, the mean change in heart rate was 8.5 beats per minute compared with 1.7 beats per minute for placebo.

(See the Use in Patients with Concomitant Illness section of PRECAUTIONS.)

Other Adverse Events Observed During the Premarketing Evaluation of Venlafaxine Hydrochloride Tablets and Venlafaxine Hydrochloride Extended-Release Capsules

During its premarketing assessment, multiple doses of venlafaxine hydrochloride extended-release capsules were administered to 705 patients in Phase 3 major depressive disorder studies and venlafaxine hydrochloride tablets were administered to 96 patients. During its premarketing assessment, multiple doses of venlafaxine hydrochloride extended-release capsules were also administered to 1381 patients in Phase 3 GAD studies, 819 patients in Phase 3 Social Anxiety Disorder studies, and 1314 patients in Phase 3 panic disorder studies. In addition, in premarketing assessment of venlafaxine hydrochloride tablets, multiple doses were administered to 2897 patients in Phase 2 to Phase 3 studies for major depressive disorder. The conditions and duration of exposure to venlafaxine in both development programs varied greatly, and included (in overlapping categories) open and double-blind studies, uncontrolled and controlled studies, inpatient (venlafaxine hydrochloride tablets only) and outpatient studies, fixed-dose, and titration studies. Untoward events associated with this exposure were recorded by clinical investigators using terminology of their own choosing. Consequently, it is not possible to provide a meaningful estimate of the proportion of individuals experiencing adverse events without first grouping similar types of untoward events into a smaller number of standardized event categories.

In the tabulations that follow, reported adverse events were classified using a standard COSTART-based Dictionary terminology. The frequencies presented, therefore, represent the proportion of the 7212 patients exposed to multiple doses of either formulation of venlafaxine who experienced an event of the type cited on at least one occasion while receiving venlafaxine. All reported events are included except those already listed in Tables 7, 8, 9, and 10 and those events for which a drug cause was remote. If the COSTART term for an event was so general as to be uninformative, it was replaced with a more informative term. It is important to emphasize that, although the events reported occurred during treatment with venlafaxine, they were not necessarily caused by it.

Events are further categorized by body system and listed in order of decreasing frequency using the following definitions: frequent adverse events are defined as those occurring on one or more occasions in at least 1/100 patients; infrequent adverse events are those occurring in 1/100 to 1/1000 patients; rare events are those occurring in fewer than 1/1000 patients.

Body as a whole - Frequent: chest pain substernal, chills, fever, neck pain; Infrequent: face edema, intentional injury, malaise, moniliasis, neck rigidity, pelvic pain, photosensitivity reaction, suicide attempt, withdrawal syndrome; Rare: appendicitis, bacteremia, carcinoma, cellulitis, granuloma.

Cardiovascular system - Frequent: migraine, tachycardia; Infrequent: angina pectoris, arrhythmia, bradycardia, extrasystoles, hypotension, peripheral vascular disorder (mainly cold feet and/or cold hands), postural hypotension, syncope; Rare: aortic aneurysm, arteritis, first-degree atrioventricular block, bigeminy, bundle branch block, capillary fragility, cerebral ischemia, coronary artery disease, congestive heart failure, heart arrest, hematoma, cardiovascular disorder (mitral valve and circulatory disturbance), mucocutaneous hemorrhage, myocardial infarct, pallor, sinus arrhythmia, thrombophlebitis.

Digestive system - Frequent: increased appetite; Infrequent: bruxism, colitis, dysphagia, tongue edema, eructation, esophagitis, gastritis, gastroenteritis, gastrointestinal ulcer, gingivitis, glossitis, rectal hemorrhage, hemorrhoids, melena, oral moniliasis, stomatitis, mouth ulceration; Rare: abdominal distension, biliary pain, cheilitis, cholecystitis, cholelithiasis, esophageal spasms, duodenitis, hematemesis, gastroesophageal reflux disease, gastrointestinal hemorrhage, gum hemorrhage, hepatitis, ileitis, jaundice, intestinal obstruction, liver tenderness, parotitis, periodontitis, proctitis, rectal disorder, salivary gland enlargement, increased salivation, soft stools, tongue discoloration.

Endocrine system - Rare: galactorrhoea, goiter, hyperthyroidism, hypothyroidism, thyroid nodule, thyroiditis.

Hemic and lymphatic system - Frequent: ecchymosis; Infrequent: anemia, leukocytosis, leukopenia, lymphadenopathy, thrombocythemia; Rare: basophilia, bleeding time increased, cyanosis, eosinophilia, lymphocytosis, multiple myeloma, purpura, thrombocytopenia.

Metabolic and nutritional - Frequent: edema, weight gain; Infrequent: alkaline phosphatase increased, dehydration, hypercholesteremia, hyperglycemia, hyperlipidemia, hypokalemia, SGOT (AST) increased, SGPT (ALT) increased, thirst; Rare: alcohol intolerance, bilirubinemia, BUN increased, creatinine increased, diabetes mellitus, glycosuria, gout, healing abnormal, hemochromatosis, hypercalcinuria, hyperkalemia, hyperphosphatemia, hyperuricemia, hypocholesteremia, hypoglycemia, hyponatremia, hypophosphatemia, hypoproteinemia, uremia.

Musculoskeletal system - Infrequent: arthritis, arthrosis, bone spurs, bursitis, leg cramps, myasthenia, tenosynovitis; Rare: bone pain, pathological fracture, muscle cramp, muscle spasms, musculoskeletal stiffness, myopathy, osteoporosis, osteosclerosis, plantar fasciitis, rheumatoid arthritis, tendon rupture.

Nervous system - Frequent: amnesia, confusion, depersonalization, hypesthesia, thinking abnormal, trismus, vertigo; Infrequent: akathisia, apathy, ataxia, circumoral paresthesia, CNS stimulation, emotional lability, euphoria, hallucinations, hostility, hyperesthesia, hyperkinesia, hypotonia, incoordination, libido increased, manic reaction, myoclonus, neuralgia, neuropathy, psychosis, seizure, abnormal speech, stupor, suicidal ideation; Rare: abnormal/changed behavior, adjustment disorder, akinesia, alcohol abuse, aphasia, bradykinesia, buccoglossal syndrome, cerebrovascular accident, feeling drunk, loss of consciousness, delusions, dementia, dystonia, energy increased, facial paralysis, abnormal gait, Guillain-Barre Syndrome, homicidal ideation, hyperchlorhydria, hypokinesia, hysteria, impulse control difficulties, motion sickness, neuritis, nystagmus, paranoid reaction, paresis, psychotic depression, reflexes decreased, reflexes increased, torticollis.

Respiratory system - Frequent: cough increased, dyspnea; Infrequent: asthma, chest congestion, epistaxis, hyperventilation, laryngismus, laryngitis, pneumonia, voice alteration; Rare: atelectasis, hemoptysis, hypoventilation, hypoxia, larynx edema, pleurisy, pulmonary embolus, sleep apnea.

Skin and appendages - Frequent: pruritus; Infrequent: acne, alopecia, contact dermatitis, dry skin, eczema, maculopapular rash, psoriasis, urticaria; Rare: brittle nails, erythema nodosum, exfoliative dermatitis, lichenoid dermatitis, hair discoloration, skin discoloration, furunculosis, hirsutism, leukoderma, miliaria, petechial rash, pruritic rash, pustular rash, vesiculobullous rash, seborrhea, skin atrophy, skin hypertrophy, skin striae, sweating decreased.

Special senses - Frequent: abnormality of accommodation, mydriasis, taste perversion; Infrequent: conjunctivitis, diplopia, dry eyes, eye pain, otitis media, parosmia, photophobia, taste loss; Rare: blepharitis, cataract, chromatopsia, conjunctival edema, corneal lesion, deafness, exophthalmos, eye hemorrhage, angle-closure glaucoma, retinal hemorrhage, subconjunctival hemorrhage, hyperacusis, keratitis, labyrinthitis, miosis, papilledema, decreased pupillary reflex, otitis externa, scleritis, uveitis, visual field defect.

Urogenital system - Frequent: albuminuria, urination impaired; Infrequent: amenorrhea,* cystitis, dysuria, hematuria, kidney calculus, kidney pain, leukorrhea,* menorrhagia,* metrorrhagia,* nocturia, breast pain, polyuria, pyuria, prostatic disorder (prostatitis, enlarged prostate, and prostate irritability,* urinary incontinence, urinary retention, urinary urgency, vaginal hemorrhage,* vaginitis*; Rare: abortion,* anuria, breast discharge, breast engorgement, balanitis,* breast enlargement, endometriosis,* female lactation,* fibrocystic breast, calcium crystalluria, cervicitis,* orchitis,* ovarian cyst,* bladder pain, prolonged erection,* gynecomastia (male),* hypomenorrhea,* kidney function abnormal, mastitis, menopause,* pyelonephritis, oliguria, salpingitis,* urolithiasis, uterine hemorrhage,* uterine spasm,* vaginal dryness.*

* Based on the number of men and women as appropriate.

Postmarketing ReportsAdverse Events

Voluntary reports of other adverse events temporally associated with the use of venlafaxine that have been received since market introduction and that may have no causal relationship with the use of venlafaxine include the following: agranulocytosis, anaphylaxis, angioedema, aplastic anemia, catatonia, congenital anomalies, impaired coordination and balance, CPK increased, deep vein thrombophlebitis, delirium, EKG abnormalities such as QT prolongation; cardiac arrhythmias including atrial fibrillation, supraventricular tachycardia, ventricular extrasystoles, and rare reports of ventricular fibrillation and ventricular tachycardia, including torsade de pointes; toxic epidermal necrolysis/Stevens-Johnson Syndrome, erythema multiforme, extrapyramidal symptoms (including dyskinesia and tardive dyskinesia), angle-closure glaucoma, hemorrhage (including eye and gastrointestinal bleeding), hepatic events (including GGT elevation; abnormalities of unspecified liver function tests; liver damage, necrosis, or failure; and fatty liver), interstitial lung disease, involuntary movements, LDH increased, neutropenia, night sweats, pancreatitis, pancytopenia, panic, prolactin increased, renal failure, rhabdomyolysis, shock-like electrical sensations or tinnitus (in some cases, subsequent to the discontinuation of venlafaxine or tapering of dose), and syndrome of inappropriate antidiuretic hormone secretion (usually in the elderly).

Drug Interactions

There have been reports of elevated clozapine levels that were temporally associated with adverse events, including seizures, following the addition of venlafaxine. There have been reports of increases in prothrombin time, partial thromboplastin time, or INR when venlafaxine was given to patients receiving warfarin therapy.

DRUG ABUSE AND DEPENDENCE SECTION

Controlled Substance Class

Venlafaxine hydrochloride extended-release capsules are not a controlled substance.

Physical and Psychological Dependence

In vitro studies revealed that venlafaxine has virtually no affinity for opiate, benzodiazepine, phencyclidine (PCP), or N-methyl-D-aspartic acid (NMDA) receptors.

Venlafaxine was not found to have any significant CNS stimulant activity in rodents. In primate drug discrimination studies, venlafaxine showed no significant stimulant or depressant abuse liability.

Discontinuation effects have been reported in patients receiving venlafaxine (see DOSAGE AND ADMINISTRATION).

While venlafaxine has not been systematically studied in clinical trials for its potential for abuse, there was no indication of drug-seeking behavior in the clinical trials. However, it is not possible to predict on the basis of premarketing experience the extent to which a CNS active drug will be misused, diverted, and/or abused once marketed. Consequently, physicians should carefully evaluate patients for history of drug abuse and follow such patients closely, observing them for signs of misuse or abuse of venlafaxine (eg, development of tolerance, incrementation of dose, drug-seeking behavior).

Close

OVERDOSAGE SECTION

Human Experience

Among the patients included in the premarketing evaluation of venlafaxine hydrochloride extended-release capsules, there were 2 reports of acute overdosage with venlafaxine hydrochloride extended-release capsules in major depressive disorder trials, either alone or in combination with other drugs. One patient took a combination of 6 g of venlafaxine hydrochloride extended-release capsules and 2.5 mg of lorazepam. This patient was hospitalized, treated symptomatically, and recovered without any untoward effects. The other patient took 2.85 g of venlafaxine hydrochloride extended-release capsules. This patient reported paresthesia of all four limbs but recovered without sequelae.

There were 2 reports of acute overdose with venlafaxine hydrochloride extended-release capsules in GAD trials. One patient took a combination of 0.75 g of venlafaxine hydrochloride extended-release capsules and 200 mg of paroxetine and 50 mg of zolpidem. This patient was described as being alert, able to communicate, and a little sleepy. This patient was hospitalized, treated with activated charcoal, and recovered without any untoward effects. The other patient took 1.2 g of venlafaxine hydrochloride extended-release capsules. This patient recovered and no other specific problems were found. The patient had moderate dizziness, nausea, numb hands and feet, and hot-cold spells 5 days after the overdose. These symptoms resolved over the next week.

There were no reports of acute overdose with venlafaxine hydrochloride extended-release capsules in Social Anxiety Disorder trials.

There were 2 reports of acute overdose with venlafaxine hydrochloride extended-release capsules in panic disorder trials. One patient took 0.675 g of venlafaxine hydrochloride extended-release capsules once, and the other patient took 0.45 g of venlafaxine hydrochloride extended-release capsules for 2 days. No signs or symptoms were associated with either overdose, and no actions were taken to treat them.

Among the patients included in the premarketing evaluation with venlafaxine hydrochloride tablets (immediate release), there were 14 reports of acute overdose with venlafaxine, either alone or in combination with other drugs and/or alcohol. The majority of the reports involved ingestion in which the total dose of venlafaxine taken was estimated to be no more than several-fold higher than the usual therapeutic dose. The 3 patients who took the highest doses were estimated to have ingested approximately 6.75 g, 2.75 g, and 2.5 g. The resultant peak plasma levels of venlafaxine for the latter 2 patients were 6.24 and 2.35 μg/mL, respectively, and the peak plasma levels of O-desmethylvenlafaxine were 3.37 and 1.30 μg/mL, respectively. Plasma venlafaxine levels were not obtained for the patient who ingested 6.75 g of venlafaxine. All 14 patients recovered without sequelae. Most patients reported no symptoms. Among the remaining patients, somnolence was the most commonly reported symptom. The patient who ingested 2.75 g of venlafaxine was observed to have 2 generalized convulsions and a prolongation of QTc to 500 msec, compared with 405 msec at baseline. Mild sinus tachycardia was reported in 2 of the other patients.

In postmarketing experience, overdose with venlafaxine has occurred predominantly in combination with alcohol and/or other drugs. The most commonly reported events in overdosage include tachycardia, changes in level of consciousness (ranging from somnolence to coma), mydriasis, seizures, and vomiting. Electrocardiogram changes (eg, prolongation of QT interval, bundle branch block, QRS prolongation), ventricular tachycardia, bradycardia, hypotension, rhabdomyolysis, vertigo, liver necrosis, serotonin syndrome, and death have been reported.

Published retrospective studies report that venlafaxine overdosage may be associated with an increased risk of fatal outcomes compared to that observed with SSRI antidepressant products, but lower than that for tricyclic antidepressants. Epidemiological studies have shown that venlafaxine-treated patients have a higher pre-existing burden of suicide risk factors than SSRI-treated patients. The extent to which the finding of an increased risk of fatal outcomes can be attributed to the toxicity of venlafaxine in overdosage as opposed to some characteristic(s) of venlafaxine-treated patients is not clear. Prescriptions for venlafaxine hydrochloride extended-release capsules should be written for the smallest quantity of capsules consistent with good patient management, in order to reduce the risk of overdose.

Management of Overdosage

Treatment should consist of those general measures employed in the management of overdosage with any antidepressant.

Ensure an adequate airway, oxygenation, and ventilation. Monitor cardiac rhythm and vital signs. General supportive and symptomatic measures are also recommended. Induction of emesis is not recommended. Gastric lavage with a large bore orogastric tube with appropriate airway protection, if needed, may be indicated if performed soon after ingestion or in symptomatic patients.

Activated charcoal should be administered. Due to the large volume of distribution of this drug, forced diuresis, dialysis, hemoperfusion, and exchange transfusion are unlikely to be of benefit. No specific antidotes for venlafaxine are known.

In managing overdosage, consider the possibility of multiple drug involvement. The physician should consider contacting a poison control center for additional information on the treatment of any overdose. Telephone numbers for certified poison control centers are listed in the Physicians' Desk Reference (PDR).

DOSAGE & ADMINISTRATION SECTION

Venlafaxine hydrochloride extended-release capsules should be administered in a single dose with food either in the morning or in the evening at approximately the same time each day. Each capsule should be swallowed whole with fluid and not divided, crushed, chewed, or placed in water, or it may be administered by carefully opening the capsule and sprinkling the entire contents on a spoonful of applesauce. This drug/food mixture should be swallowed immediately without chewing and followed with a glass of water to ensure complete swallowing of the pellets.

Initial TreatmentMajor Depressive Disorder

For most patients, the recommended starting dose for venlafaxine hydrochloride extended-release capsules is 75 mg/day, administered in a single dose. In the clinical trials establishing the efficacy of venlafaxine hydrochloride extended-release capsules in moderately depressed outpatients, the initial dose of venlafaxine was 75 mg/day. For some patients, it may be desirable to start at 37.5 mg/day for 4 to 7 days, to allow new patients to adjust to the medication before increasing to 75 mg/day. While the relationship between dose and antidepressant response for venlafaxine hydrochloride extended-release capsules has not been adequately explored, patients not responding to the initial 75 mg/day dose may benefit from dose increases to a maximum of approximately 225 mg/day. Dose increases should be in increments of up to 75 mg/day, as needed, and should be made at intervals of not less than 4 days, since steady state plasma levels of venlafaxine and its major metabolites are achieved in most patients by day 4. In the clinical trials establishing efficacy, upward titration was permitted at intervals of 2 weeks or more; the average doses were about 140 to 180 mg/day (see Clinical Trials under CLINICAL PHARMACOLOGY).

It should be noted that, while the maximum recommended dose for moderately depressed outpatients is also 225 mg/day for venlafaxine hydrochloride tablets (immediate release), more severely depressed inpatients in one study of the development program for that product responded to a mean dose of 350 mg/day (range of 150 to 375 mg/day). Whether or not higher doses of venlafaxine hydrochloride extended-release capsules are needed for more severely depressed patients is unknown; however, the experience with venlafaxine hydrochloride extended-release capsule doses higher than 225 mg/day is very limited. (See PRECAUTIONS-General-Use in Patients with Concomitant Illness.)

Generalized Anxiety Disorder

For most patients, the recommended starting dose for venlafaxine hydrochloride extended-release capsules are 75 mg/day, administered in a single dose. In clinical trials establishing the efficacy of venlafaxine hydrochloride extended-release capsules in outpatients with Generalized Anxiety Disorder (GAD), the initial dose of venlafaxine was 75 mg/day. For some patients, it may be desirable to start at 37.5 mg/day for 4 to 7 days, to allow new patients to adjust to the medication before increasing to 75 mg/day. Although a dose-response relationship for effectiveness in GAD was not clearly established in fixed-dose studies, certain patients not responding to the initial 75 mg/day dose may benefit from dose increases to a maximum of approximately 225 mg/day. Dose increases should be in increments of up to 75 mg/day, as needed, and should be made at intervals of not less than 4 days. (See the Use in Patients with Concomitant Illness section of PRECAUTIONS.)

Social Anxiety Disorder (Social Phobia)

The recommended dose is 75 mg/day, administered in a single dose. There was no evidence that higher doses confer any additional benefit. (See the Use in Patients with Concomitant Illness section of PRECAUTIONS.)

Panic Disorder

It is recommended that initial single doses of 37.5 mg/day of venlafaxine hydrochloride extended-release capsules be used for 7 days. In clinical trials establishing the efficacy of venlafaxine hydrochloride extended-release capsules in outpatients with panic disorder, initial doses of 37.5 mg/day for 7 days were followed by doses of 75 mg/day and subsequent weekly dose increases of 75 mg/day to a maximum dose of 225 mg/day. Although a dose-response relationship for effectiveness in patients with panic disorder was not clearly established in fixed-dose studies, certain patients not responding to 75 mg/day may benefit from dose increases to a maximum of approximately 225 mg/day. Dose increases should be in increments of up to 75 mg/day, as needed, and should be made at intervals of not less than 7 days. (See the Use in Patients with Concomitant Illness section of PRECAUTIONS.)

Switching Patients from Venlafaxine Hydrochloride Tablets

Depressed patients who are currently being treated at a therapeutic dose with venlafaxine hydrochloride tablets (immediate release) may be switched to venlafaxine hydrochloride extended-release capsules at the nearest equivalent dose (mg/day), eg, 37.5 mg venlafaxine two-times-a-day to 75 mg venlafaxine hydrochloride extended-release capsules once daily. However, individual dosage adjustments may be necessary.

Switching a Patient To or From a Monoamine Oxidase Inhibitor (MAOI) Intended to Treat Psychiatric Disorders

At least 14 days should elapse between discontinuation of an MAOI intended to treat psychiatric disorders and initiation of therapy with venlafaxine hydrochloride extended-release capsules. Conversely, at least 7 days should be allowed after stopping venlafaxine hydrochloride extended-release capsules before starting an MAOI intended to treat psychiatric disorders (see CONTRAINDICATIONS).

Use of Venlafaxine Hydrochloride Extended-Release Capsules With Other MAOls, Such as Linezolid or Methylene Blue

Do not start venlafaxine hydrochloride extended-release capsules in a patient who is being treated with linezolid or intravenous methylene blue because there is increased risk of serotonin syndrome. In a patient who requires more urgent treatment of a psychiatric condition, other interventions, including hospitalization, should be considered (see CONTRAINDICATIONS).

In some cases, a patient already receiving therapy with venlafaxine hydrochloride extended-release capsules may require urgent treatment with linezolid or intravenous methylene blue. If acceptable alternatives to linezolid or intravenous methylene blue treatment are not available and the potential benefits of linezolid or intravenous methylene blue treatment are judged to outweigh the risks of serotonin syndrome in a particular patient, venlafaxine hydrochloride extended-release capsules should be stopped promptly, and linezolid or intravenous methylene blue can be administered. The patient should be monitored for symptoms of serotonin syndrome for 7 days or until 24 hours after the last dose of linezolid or intravenous methylene blue, whichever comes first. Therapy with venlafaxine hydrochloride extended-release capsules may be resumed 24 hours after the last dose of linezolid or intravenous methylene blue (see WARNINGS).

The risk of administering methylene blue by non-intravenous routes (such as oral tablets or by local injection) or in intravenous doses much lower than 1 mg/kg with venlafaxine hydrochloride extended-release capsules is unclear. The clinician should, nevertheless, be aware of the possibility of emergent symptoms of serotonin syndrome with such use (see WARNINGS).

Special PopulationsTreatment of Pregnant Women During the Third Trimester

Neonates exposed to venlafaxine hydrochloride extended-release capsules, other SNRIs, or SSRIs, late in the third trimester have developed complications requiring prolonged hospitalization, respiratory support, and tube feeding (see PRECAUTIONS). When treating pregnant women with venlafaxine hydrochloride extended-release capsules during the third trimester, the physician should carefully consider the potential risks and benefits of treatment.

Patients with Hepatic Impairment

Given the decrease in clearance and increase in elimination half-life for both venlafaxine and ODV that is observed in patients with hepatic cirrhosis and mild and moderate hepatic impairment compared with normal subjects (see CLINICAL PHARMACOLOGY), it is recommended that the total daily dose be reduced by 50% in patients with mild to moderate hepatic impairment. Since there was much individual variability in clearance between subjects with cirrhosis, it may be necessary to reduce the dose even more than 50%, and individualization of dosing may be desirable in some patients.

Patients with Renal Impairment

Given the decrease in clearance for venlafaxine and the increase in elimination half-life for both venlafaxine and ODV that is observed in patients with renal impairment (GFR = 10 to 70 mL/min) compared with normal subjects (see CLINICAL PHARMACOLOGY), it is recommended that the total daily dose be reduced by 25% to 50%. In patients undergoing hemodialysis, it is recommended that the total daily dose be reduced by 50%. Because there was much individual variability in clearance between patients with renal impairment, individualization of dosage may be desirable in some patients.

Elderly Patients

No dose adjustment is recommended for elderly patients solely on the basis of age. As with any drug for the treatment of major depressive disorder, Generalized Anxiety Disorder, Social Anxiety Disorder, or panic disorder, however, caution should be exercised in treating the elderly. When individualizing the dosage, extra care should be taken when increasing the dose.

Maintenance Treatment

There is no body of evidence available from controlled trials to indicate how long patients with major depressive disorder, Generalized Anxiety Disorder, Social Anxiety Disorder, or panic disorder, should be treated with venlafaxine hydrochloride extended-release capsules.

It is generally agreed that acute episodes of major depressive disorder require several months or longer of sustained pharmacological therapy beyond response to the acute episode. In one study, in which patients responding during 8 weeks of acute treatment with venlafaxine hydrochloride extended-release capsules were assigned randomly to placebo or to the same dose of venlafaxine hydrochloride extended-release capsules (75, 150, or 225 mg/day, qAM) during 26 weeks of maintenance treatment as they had received during the acute stabilization phase, longer-term efficacy was demonstrated. A second longer-term study has demonstrated the efficacy of venlafaxine hydrochloride tablets in maintaining a response in patients with recurrent major depressive disorder who had responded and continued to be improved during an initial 26 weeks of treatment and were then randomly assigned to placebo or venlafaxine hydrochloride tablets for periods of up to 52 weeks on the same dose (100 to 200 mg/day, on a b.i.d. schedule) (see Clinical Trials under CLINICAL PHARMACOLOGY). Based on these limited data, it is not known whether or not the dose of venlafaxine hydrochloride extended-release capsules needed for maintenance treatment is identical to the dose needed to achieve an initial response. Patients should be periodically reassessed to determine the need for maintenance treatment and the appropriate dose for such treatment.

In patients with Generalized Anxiety Disorder, venlafaxine hydrochloride extended-release capsules have been shown to be effective in 6-month clinical trials. The need for continuing medication in patients with GAD who improve with venlafaxine hydrochloride extended-release capsule treatment should be periodically reassessed.

In patients with Social Anxiety Disorder, venlafaxine hydrochloride extended-release capsules have been shown to be effective in a 6-month clinical trial. The need for continuing medication in patients with Social Anxiety Disorder who improve with venlafaxine hydrochloride extended-release capsule treatment should be periodically reassessed.

In a study of panic disorder in which patients responding during 12 weeks of acute treatment with venlafaxine hydrochloride extended-release capsules were assigned randomly to placebo or to the same dose of venlafaxine hydrochloride extended-release capsules (75, 150, or 225 mg/day), patients continuing venlafaxine hydrochloride extended-release capsules experienced a significantly longer time to relapse than patients randomized to placebo. The need for continuing medication in patients with panic disorder who improve with venlafaxine hydrochloride extended-release capsules treatment should be periodically reassessed.

Discontinuing Venlafaxine Hydrochloride Extended-Release Capsules

Symptoms associated with discontinuation of venlafaxine hydrochloride extended-release capsules, other SNRIs, and SSRIs, have been reported (see PRECAUTIONS). Patients should be monitored for these symptoms when discontinuing treatment. A gradual reduction in the dose rather than abrupt cessation is recommended whenever possible. If intolerable symptoms occur following a decrease in the dose or upon discontinuation of treatment, then resuming the previously prescribed dose may be considered. Subsequently, the physician may continue decreasing the dose but at a more gradual rate. In clinical trials with venlafaxine hydrochloride extended-release capsules, tapering was achieved by reducing the daily dose by 75 mg at 1 week intervals. Individualization of tapering may be necessary.

HOW SUPPLIED SECTION

Venlafaxine hydrochloride extended-release capsules are available as follows:

37.5 mg, grey cap/peach body with W and “Effexor XR” on the cap and “37.5” on the body.

NDC 60505-3778-3, bottle of 30 capsules in unit of use package. NDC 60505-3778-9, bottle of 90 capsules in unit of use package.

75 mg, peach cap and body with W and “Effexor XR” on the cap and “75” on the body.

NDC 60505-3779-3, bottle of 30 capsules in unit of use package. NDC 60505-3779-9, bottle of 90 capsules in unit of use package.

150 mg, dark orange cap and body with W and “Effexor XR” on the cap and “150” on the body.

NDC 60505-3780-3, bottle of 30 capsules in unit of use package. NDC 60505-3780-9, bottle of 90 capsules in unit of use package.

Store at controlled room temperature, 20° to 25°C (68° to 77°F).

The unit of use package is intended to be dispensed as a unit.

Distributed by:

Apotex Corp.

Weston, Florida 33326

LAB-0501-14.0

SPL MEDGUIDE SECTION

VENLAFAXINE XR

(venlafaxine hydrochloride)

(Extended-Release Capsules)

Read the Medication Guide that comes with VENLAFAXINE XR before you start taking it and each time you get a refill. There may be new information. This Medication Guide does not take the place of talking to your healthcare provider about your medical condition or treatment. Talk with your healthcare provider if there is something you do not understand or want to learn more about.

What is the most important information I should know about VENLAFAXINE XR?

VENLAFAXINE XR and other antidepressant medicines may cause serious side effects, including:

1.Suicidal thoughts or actions:

- VENLAFAXINE XR and other antidepressant medicines may increase suicidal thoughts or actions in some children, teenagers, or young adults within the first few months of treatment or when the dose is changed.
- Depression or other serious mental illnesses are the most important causes of suicidal thoughts or actions.
- Watch for these changes and call your healthcare provider right away if you notice:
  - New or sudden changes in mood, behavior, actions, thoughts, or feelings, especially if severe.
  - Pay particular attention to such changes when VENLAFAXINE XR is started or when the dose is changed.
  Keep all follow-up visits with your healthcare provider and call between visits if you are worried about symptoms.
  Call your healthcare provider right away if you have any of the following symptoms, or call 911 if an emergency, especially if they are new, worse, or worry you:
  - attempts to commit suicide
  - acting on dangerous impulses
  - acting aggressive or violent
  - thoughts about suicide or dying
  - new or worse depression
  - new or worse anxiety or panic attacks
  - feeling agitated, restless, angry or irritable
  - trouble sleeping
  - an increase in activity or talking more than what is normal for you
  - other unusual changes in behavior or mood
  - Visual problems
    - eye pain
    - changes in vision
    - swelling or redness in or around the eye
    Only some people are at risk for these problems. You may want to undergo an eye examination to see if you are at risk and receive preventative treatment if you are.

Call your healthcare provider right away if you have any of the following symptoms, or call 911 if an emergency. VENLAFAXINE XR may be associated with these serious side effects:

2.Serotonin Syndrome

This condition can be life-threatening and may include:

- agitation, hallucinations, coma or other changes in mental status
- coordination problems or muscle twitching (overactive reflexes)
- racing heartbeat, high or low blood pressure
- sweating or fever
- nausea, vomiting, or diarrhea
- muscle rigidity

3.Changes in blood pressure. VENLAFAXINE XR may:

- increase your blood pressure. Control high blood pressure before starting treatment and monitor blood pressure regularly

4.Enlarged pupils (mydriasis).5.Anxiety and insomnia.6.Changes in appetite or weight.7.Manic/hypomanic episodes:

- greatly increased energy
- severe trouble sleeping
- racing thoughts
- reckless behavior
- unusually grand ideas
- excessive happiness or irritability
- talking more or faster than usual

8.Low salt (sodium) levels in the blood. Elderly people may be at greater risk for this. Symptoms may include:

- headache
- weakness or feeling unsteady
- confusion, problems concentrating or thinking or memory problems

9.Seizures or convulsions.10.Abnormal bleeding: VENLAFAXINE XR and other antidepressant medicines may increase your risk of bleeding or bruising, especially if you take the blood thinner warfarin (Coumadin ®, Jantoven ®), a non-steroidal anti-inflammatory drug (NSAIDs, like ibuprofen or naproxen), or aspirin.11.Elevated cholesterol.12.Lung disease and pneumonia: VENLAFAXINE XR may cause rare lung problems. Symptoms include:

- worsening shortness of breath
- cough
- chest discomfort

13.Severe allergic reactions:

- trouble breathing
- swelling of the face, tongue, eyes or mouth
- rash, itchy welts (hives) or blisters, alone or with fever or joint pain

Do not stop VENLAFAXINE XR without first talking to your healthcare provider. Stopping VENLAFAXINE XR too quickly or changing from another antidepressant too quickly may cause serious symptoms including:

- anxiety, irritability
- feeling tired, restless or problems sleeping
- headache, sweating, dizziness
- electric shock-like sensations, shaking, confusion, nightmares
- vomiting, nausea, diarrhea

What is VENLAFAXINE XR?

VENLAFAXINE XR is a prescription medicine used to treat depression. It is important to talk with your healthcare provider about the risks of treating depression and also the risks of not treating it. You should discuss all treatment choices with your healthcare provider.

VENLAFAXINE XR is also used to treat:

- Generalized Anxiety Disorder (GAD)
- Social Anxiety Disorder (SAD)
- Panic Disorder (PD)

Talk to your healthcare provider if you do not think that your condition is getting better with VENLAFAXINE XR treatment.

Who should not take VENLAFAXINE XR?

Do not take VENLAFAXINE XR if you:

- are allergic to VENLAFAXINE XR or any of the ingredients in VENLAFAXINE XR. See the end of this Medication Guide for a complete list of ingredients in VENLAFAXINE XR.
- have uncontrolled angle-closure glaucoma
- take a Monoamine Oxidase Inhibitor (MAOI). Ask your healthcare provider or pharmacist if you are not sure if you take an MAOI, including the antibiotic linezolid.
  - Do not take an MAOI within 7 days of stopping VENLAFAXINE XR unless directed to do so by your physician.
  - Do not start VENLAFAXINE XR if you stopped taking an MAOI in the last 2 weeks unless directed to do so by your physician.
  People who take VENLAFAXINE XR close in time to an MAOI may have serious or even life-threatening side effects. Get medical help right away if you have any of these symptoms:
  - high fever
  - uncontrolled muscle spasms
  - stiff muscles
  - rapid changes in heart rate or blood pressure
  - confusion
  - loss of consciousness (pass out)

What should I tell my healthcare provider before taking VENLAFAXINE XR? Ask if you are not sure.

Before starting VENLAFAXINE XR, tell your healthcare provider if you:

- Are taking certain drugs such as:
  - Medicines used to treat migraine headaches such as:
    - triptans
  - Medicines used to treat mood, anxiety, psychotic or thought disorders, such as:
    - tricyclic antidepressants
    - lithium
    - SSRIs
    - SNRIs
    - antipsychotic drugs
  - Medicines used to treat pain such as:
    - tramadol
  - Medicines used to thin your blood such as:
    - warfarin
  - Medicines used to treat heartburn such as:
    - Cimetidine
  - Over-the-counter medicines or supplements such as:
    - Aspirin or other NSAIDs
    - Tryptophan
    - St. John's Wort
- have heart problems
- have diabetes
- have liver problems
- have kidney problems
- have thyroid problems
- have or had seizures or convulsions
- have bipolar disorder or mania
- have low sodium levels in your blood
- have high blood pressure
- have high cholesterol
- have or had bleeding problems
- are pregnant or plan to become pregnant. It is not known if VENLAFAXINE XR will harm your unborn baby. Talk to your healthcare provider about the benefits and risks of treating depression during pregnancy
- are breast-feeding or plan to breast-feed. Some VENLAFAXINE XR may pass into your breast milk. Talk to your healthcare provider about the best way to feed your baby while taking VENLAFAXINE XR.

Tell your healthcare provider about all the medicines that you take, including prescription and non-prescription medicines, vitamins, and herbal supplements. VENLAFAXINE XR and some medicines may interact with each other, may not work as well, or may cause serious side effects.

Your healthcare provider or pharmacist can tell you if it is safe to take VENLAFAXINE XR with your other medicines. Do not start or stop any medicine while taking VENLAFAXINE XR without talking to your healthcare provider first.

If you take VENLAFAXINE XR, you should not take any other medicines that contain (venlafaxine) including: venlafaxine HCl.

How should I take VENLAFAXINE XR?

- Take VENLAFAXINE XR exactly as prescribed. Your healthcare provider may need to change the dose of VENLAFAXINE XR until it is the right dose for you.
- VENLAFAXINE XR is to be taken with food.
- If you miss a dose of VENLAFAXINE XR, take the missed dose as soon as you remember. If it is almost time for the next dose, skip the missed dose and take your next dose at the regular time. Do not take two doses of VENLAFAXINE XR at the same time.
- If you take too much VENLAFAXINE XR, call your healthcare provider or poison control center right away, or get emergency treatment.
- When switching from another antidepressant to VENLAFAXINE XR your doctor may want to lower the dose of the initial antidepressant first to avoid side effects

What should I avoid while taking VENLAFAXINE XR?

VENLAFAXINE XR can cause sleepiness or may affect your ability to make decisions, think clearly, or react quickly. You should not drive, operate heavy machinery, or do other dangerous activities until you know how VENLAFAXINE XR affects you. Do not drink alcohol while using VENLAFAXINE XR.

What are the possible side effects of VENLAFAXINE XR?

VENLAFAXINE XR may cause serious side effects, including:

- See " What is the most important information I should know about VENLAFAXINE XR?"
- Increased cholesterol- have your cholesterol checked regularly
- Newborns whose mothers take VENLAFAXINE XR in the third trimester may have problems right after birth including:
  - problems feeding and breathing
  - seizures
  - shaking, jitteriness or constant crying
  - Angle-closure glaucoma

Common possible side effects in people who take VENLAFAXINE XR include:

- unusual dreams
- sexual problems
- loss of appetite, constipation, diarrhea, nausea or vomiting, or dry mouth
- feeling tired, fatigued or overly sleepy
- change in sleep habits, problems sleeping
- yawning
- tremor or shaking
- dizziness, blurred vision
- sweating
- feeling anxious, nervous or jittery
- headache
- increase in heart rate

Tell your healthcare provider if you have any side effect that bothers you or that does not go away. These are not all the possible side effects of VENLAFAXINE XR. For more information, ask your healthcare provider or pharmacist.

CALL YOUR DOCTOR FOR MEDICAL ADVICE ABOUT SIDE EFFECTS. YOU MAY REPORT SIDE EFFECTS TO THE FDA AT 1-800-FDA-1088.

How should I store VENLAFAXINE XR?

- Store VENLAFAXINE XR at room temperature between 68°F and 77°F (20°C to 25°C).
- Keep VENLAFAXINE XR in a dry place.

Keep VENLAFAXINE XR and all medicines out of the reach of children.

General information about VENLAFAXINE XR

Medicines are sometimes prescribed for purposes other than those listed in a Medication Guide. Do not use VENLAFAXINE XR for a condition for which it was not prescribed. Do not give VENLAFAXINE XR to other people, even if they have the same condition. It may harm them.

This Medication Guide summarizes the most important information about VENLAFAXINE XR. If you would like more information, talk with your healthcare provider. You may ask your healthcare provider or pharmacist for information about VENLAFAXINE XR that is written for healthcare professionals.

What are the ingredients in VENLAFAXINE XR?

Active ingredient: (venlafaxine)

Inactive ingredients:

Extended-Release Capsules: cellulose, ethylcellulose, gelatin, hypromellose, iron oxide, and titanium dioxide

This Medication Guide has been approved by the U.S. Food and Drug Administration for all antidepressants.

This product's label may have been updated. For current full prescribing information, please visit www.pfizer.com

Distributed by:

Apotex Corp.

Weston, Florida 33326

LAB-0544-4.0

May 2014

DOSAGE FORMS AND STRENGTHS

Venlafaxine Hydrochloride Extended-release Capsules, USP are available in the following strengths:

Venlafaxine Hydrochloride Extended-release Capsules USP, 37.5 mg are white to off-white free flowing pellets filled in size '3' hard gelatin capsules with grey colored cap printed with "ZA-35" in black ink & white body printed with "37.5 mg" in black ink.
Venlafaxine Hydrochloride Extended-release Capsules USP, 75 mg are white to off-white free flowing pellets filled in size '1' hard gelatin capsules with peach colored cap printed with "ZA-36" in black ink & white body printed with "75 mg" in black ink.
Venlafaxine Hydrochloride Extended-release Capsules USP, 150 mg are white to off-white free flowing pellets filled in size '0' hard gelatin capsules with dark orange colored cap printed with "ZA-37" in black ink & white body printed with "150 mg" in black ink.

DRUG INTERACTIONS

7.1 Central Nervous System (CNS)-Active Drugs

The risk of using venlafaxine in combination with other CNS-active drugs has not been systematically evaluated. Consequently, caution is advised when venlafaxine hydrochloride extended-release capsules are taken in combination with other CNS- active drugs.

7.2 Monoamine Oxidase Inhibitors

Adverse reactions, some of which were serious, have been reported in patients who have recently been discontinued from an MAOI and started on antidepressants with pharmacological properties similar to venlafaxine hydrochloride extended-release capsules (SNRIs or SSRIs), or who have recently had SNRI or SSRI therapy discontinued prior to initiation of an MAOI [see Dosage and Administration (2.9), Contraindications (4.2) and Warnings and Precautions (5.2)].

7.3 Serotonergic Drugs

Based on the mechanism of action of venlafaxine hydrochloride extended-release capsules and the potential for serotonin syndrome, caution is advised when venlafaxine hydrochloride extended-release capsules are coadministered with other drugs that may affect the serotonergic neurotransmitter systems, such as triptans, SSRIs, other SNRIs, linezolid (an antibiotic which is a reversible non-selective MAOI), lithium, tramadol, or St. John's wort. If concomitant treatment with venlafaxine hydrochloride extended-release capsules and these drugs is clinically warranted, careful observation of the patient is advised, particularly during treatment initiation and dose increases. The concomitant use of venlafaxine hydrochloride extended-release capsules with tryptophan supplements is not recommended [see Dosage and Administration (2.9), Contraindications (4.2), and Warnings and Precautions (5.2)].

7.4 Drugs that Interfere with Hemostasis (e.g., NSAIDs, Aspirin, and Warfarin)

Serotonin release by platelets plays an important role in hemostasis. The use of psychotropic drugs that interfere with serotonin reuptake is associated with the occurrence of upper gastrointestinal bleeding and concurrent use of an NSAID or aspirin may potentiate this risk of bleeding [see Warnings and Precautions (5.4)]. Altered anticoagulant effects, including increased bleeding, have been reported when SSRIs and SNRIs are coadministered with warfarin. Patients receiving warfarin therapy should be carefully monitored when venlafaxine hydrochloride extended-release capsules are initiated or discontinued.

7.5 Weight Loss Agents

The safety and efficacy of venlafaxine therapy in combination with weight loss agents, including phentermine, have not been established. Coadministration of venlafaxine hydrochloride extended-release capsules and weight loss agents is not recommended. Venlafaxine hydrochloride extended-release capsules are not indicated for weight loss alone or in combination with other products.

7.6 Effects of Other Drugs on Venlafaxine Hydrochloride Extended-release Capsules

Figure 1: Effect of interacting drugs on the pharmacokinetics of venlafaxine and active metabolite

[Venlafaxine hydrochloride extended-release capsules, USP]

Abbreviations: ODV, O-desmethylvenlafaxine; AUC, area under the curve; Cmax, peak plasma concentrations; EM's, extensive metabolizers; PM's, poor metabolizers

* No dose adjustment on coadministration with CYP2D6 inhibitors (Fig 3 and Metabolism Section 12.3)

7.7 Effects of Venlafaxine Hydrochloride Extended-release Capsules on Other Drugs

Figure 2: Effect of venlafaxine on the pharmacokinetics interacting drugs and their active metabolites.

[Venlafaxine hydrochloride extended-release capsules, USP]

Abbreviations: AUC, area under the curve; Cmax, peak plasma concentrations; OH, hydroxyl

* Data for 2-OH desipramine were not plotted to enhance clarity; the fold change and 90% CI for Cmax and AUC of 2-OH desipramine were 6.6 (5.5, 7.9) and 4.4 (3.8, 5), respectively.

Note:

*: Administration of venlafaxine in a stable regimen did not exaggerate the psychomotor and psychometric effects induced by ethanol in these same subjects when they were not receiving venlafaxine.

7.8 Drug-Laboratory Test Interactions

False-positive urine immunoassay screening tests for phencyclidine (PCP) and amphetamine have been reported in patients taking venlafaxine. This is due to lack of specificity of the screening tests. False positive test results may be expected for several days following discontinuation of venlafaxine therapy. Confirmatory tests, such as gas chromatography/mass spectrometry, will distinguish venlafaxine from PCP and amphetamine.

USE IN SPECIFIC POPULATIONS

8.1 Pregnancy

Teratogenic Effects – Pregnancy Category C

Venlafaxine did not cause malformations in offspring of rats or rabbits given doses up to 2.5 times (rat) or 4 times (rabbit) the maximum recommended human daily dose on a mg/m2 basis. However, in rats, there was a decrease in pup weight, an increase in stillborn pups, and an increase in pup deaths during the first 5 days of lactation, when dosing began during pregnancy and continued until weaning. The cause of these deaths is not known. These effects occurred at 2.5 times (mg/m2) the maximum human daily dose. The no effect dose for rat pup mortality was 0.25 times the human dose on a mg/m2 basis. In reproductive developmental studies in rats and rabbits with O-desmethylvenlafaxine (ODV), the major human metabolite of venlafaxine, evidence of teratogenicity was not observed at exposure margins of 13 in rats and 0.3 in rabbits. There are no adequate and well-controlled studies in pregnant women. Venlafaxine hydrochloride extended-release capsules should be used during pregnancy only if the potential benefit justifies the potential risk to the fetus. Because animal reproduction studies are not always predictive of human response, this drug should be used during pregnancy only if clearly needed.

Non-teratogenic Effects

Neonates exposed to venlafaxine hydrochloride extended-release capsules, other SNRIs, or SSRIs, late in the third trimester have developed complications requiring prolonged hospitalization, respiratory support, and tube feeding. Such complications can arise immediately upon delivery. Reported clinical findings have included respiratory distress, cyanosis, apnea, seizures, temperature instability, feeding difficulty, vomiting, hypoglycemia, hypotonia, hypertonia, hyperreflexia, tremor, jitteriness, irritability, and constant crying. These features are consistent with either a direct toxic effect of SSRIs and SNRIs, or possibly a drug discontinuation syndrome. It should be noted, that in some cases the clinical picture is consistent with serotonin syndrome [see Warnings and Precautions (5.2) and Drug Interactions (7.3)]. When treating a pregnant woman with venlafaxine hydrochloride extended-release capsules during the third trimester, the physician should carefully consider the potential risks and benefits of treatment.

8.2 Labor and Delivery

The effect of venlafaxine on labor and delivery in humans is unknown.

8.3 Nursing Mothers

Venlafaxine and ODV have been reported to be excreted in human milk. Because of the potential for serious adverse reactions in nursing infants from venlafaxine hydrochloride extended-release capsules, a decision should be made whether to discontinue nursing or to discontinue the drug, taking into account the importance of the drug to the mother.

8.4 Pediatric Use

Two placebo-controlled trials in 766 pediatric patients with MDD and two placebo-controlled trials in 793 pediatric patients with GAD have been conducted with venlafaxine hydrochloride extended-release capsules, and the data were not sufficient to support a claim for use in pediatric patients.

Anyone considering the use of venlafaxine hydrochloride extended-release capsules in a child or adolescent must balance the potential risks with the clinical need [see Boxed Warning, Warnings and Precautions (5.1, 5.10, 5.11) and Adverse Reactions (6.4)].

Although no studies have been designed to primarily assess venlafaxine hydrochloride extended-release capsule's impact on the growth, development, and maturation of children and adolescents, the studies that have been done suggest that venlafaxine hydrochloride extended-release capsules may adversely affect weight and height [see Warnings and Precautions (5.10)]. Should the decision be made to treat a pediatric patient with venlafaxine hydrochloride extended-release capsules, regular monitoring of weight and height is recommended during treatment, particularly if treatment is to be continued long-term [see Warnings and Precautions (5.10, 5.11)]. The safety of venlafaxine hydrochloride extended-release capsules treatment for pediatric patients has not been systematically assessed for chronic treatment longer than six months in duration. In the studies conducted in pediatric patients (ages 6 to 17), the occurrence of blood pressure and cholesterol increases considered to be clinically relevant in pediatric patients was similar to that observed in adult patients. Consequently, the precautions for adults apply to pediatric patients [see Warnings and Precautions (5.3, 6.3)].

8.5 Geriatric Use

The percentage of patients in clinical studies for venlafaxine hydrochloride extended-release capsules for MDD, GAD, SAD, and PD who were 65 years of age or older are shown in Table 15.

Table 15 Percentage (and Number of Patients Studied) of Patients 65 Years of Age and Older by Indicationa

a In addition, in the premarketing assessment of venlafaxine hydrochloride tablets, 12% (357/2,897) of patients were ≥ 65 years of age.

Indication
Venlafaxine Hydrochloride Extended-release Capsules
MDD
4 (14/357)
GAD
6 (77/1,381)
SAD
1 (10/819)
PD
2 (16/1,001)

No overall differences in effectiveness or safety were observed between geriatric patients and younger patients, and other reported clinical experience generally has not identified differences in response between the elderly and younger patients. However, greater sensitivity of some older individuals cannot be ruled out. SSRIs and SNRIs, including venlafaxine hydrochloride extended-release capsules, have been associated with cases of clinically significant hyponatremia in elderly patients, who may be at greater risk for this adverse event [see Warnings and Precautions (5.9)].

The pharmacokinetics of venlafaxine and ODV are not substantially altered in the elderly [see Clinical Pharmacology (12.3)] (see Figure 3). No dose adjustment is recommended for the elderly on the basis of age alone, although other clinical circumstances, some of which may be more common in the elderly, such as renal or hepatic impairment, may warrant a dose reduction [see Dosage and Administration (2.6)].

8.6 Age and Gender

A population pharmacokinetic analysis of 404 venlafaxine hydrochloride tablets-treated patients from two studies involving both twice daily and three times daily regimens showed that dose-normalized trough plasma levels of either venlafaxine or ODV were unaltered by age or gender differences. Dosage adjustment based on the age or gender of a patient is generally not necessary [see Dosage and Administration (2.6)] (see Table 15).

8.7 Use in Patient Subgroups

Figure 3: Pharmacokinetics of venlafaxine and its metabolite O-desmethylvenlafaxine (ODV) in special populations.

[Venlafaxine hydrochloride extended-release capsules, USP]

Abbreviations: ODV, O-desmethylvenlafaxine; AUC, area under the curve; Cmax, peak plasma concentrations;

*Similar effect is expected with strong CYP2D6 inhibitors

NONCLINICAL TOXICOLOGY

13.1 Carcinogenesis, Mutagenesis, Impairment of Fertility

Carcinogenesis

Tumors were not increased by venlafaxine treatment in mice or rats. Venlafaxine was given by oral gavage to mice for 18 months at doses up to 120 mg/kg per day, which was 1.7 times the maximum recommended human dose on a mg/m2 basis. Venlafaxine was also given to rats by oral gavage for 24 months at doses up to 120 mg/kg per day. In rats receiving the 120 mg/kg dose, plasma concentrations of venlafaxine at necropsy were 1 times (male rats) and 6 times (female rats) the plasma concentrations of patients receiving the maximum recommended human dose. Plasma levels of the O-desmethyl metabolite (ODV) were lower in rats than in patients receiving the maximum recommended dose. O desmethylvenlafaxine (ODV), the major human metabolite of venlafaxine, administered by oral gavage to mice and rats for 2 years did not increase the incidence of tumors in either study. Mice received ODV at dosages up to 500/300 mg/kg/day (dosage lowered after 45 weeks of dosing). The exposure at the 300 mg/kg/day dose is 9 times that of a human dose of 225 mg/day. Rats received ODV at dosages up to 300 mg/kg/day (males) or 500 mg/kg/day (females). The exposure at the highest dose is approximately 8 (males) or 11 (females) times that of a human dose of 225 mg/day.

Mutagenesis

Venlafaxine and the major human metabolite, ODV, were not mutagenic in the Ames reverse mutation assay in Salmonella bacteria or the Chinese hamster ovary/HGPRT mammalian cell forward gene mutation assay. Venlafaxine was also not mutagenic or clastogenic in the in vitro BALB/c-3T3 mouse cell transformation assay, the sister chromatid exchange assay in cultured Chinese hamster ovary cells, or in the in vivo chromosomal aberration assay in rat bone marrow. ODV was not clastogenic in the in vitro Chinese hamster ovary cell chromosomal aberration assay or in the in vivo chromosomal aberration assay in rats.

Impairment of Fertility

Reproduction and fertility studies of venlafaxine in rats showed no adverse effects of venlafaxine on male or female fertility at oral doses of up to 2 times the maximum recommended human dose of 225 mg/day on a mg/m2 basis. However, reduced fertility was observed in a study in which male and female rats were treated with O-desmethylvenlafaxine (ODV), the major human metabolite of venlafaxine, prior to and during mating and gestation. This occurred at an ODV exposure (AUC) approximately 2 to 3 times that associated with a human venlafaxine dose of 225 mg/day.

CLINICAL STUDIES

14.1 Major Depressive Disorder

The efficacy of venlafaxine hydrochloride extended-release capsules as a treatment for Major Depressive Disorder (MDD) was established in two placebo-controlled, short-term (8 weeks for study 1; 12 weeks for study 2), flexible-dose studies, with doses starting at 75 mg per day and ranging to 225 mg per day in adult outpatients meeting DSM-III-R or DSM-IV criteria for MDD. In moderately depressed outpatients, the initial dose of venlafaxine was 75 mg per day. In both studies, venlafaxine hydrochloride extended-release capsules demonstrated superiority over placebo on the primary efficacy measure defined as change from baseline in the HAM-D-21 total score to the endpoint visit, venlafaxine hydrochloride extended-release capsules also demonstrated superiority over placebo on the key secondary efficacy endpoint, the Clinical Global Impressions (CGI) Severity of Illness scale. Examination of gender subsets of the population studied did not reveal any differential responsiveness on the basis of gender.

A 4-week study of inpatients meeting DSM-III-R criteria for MDD with melancholia utilizing venlafaxine hydrochloride tablets in a range of 150 to 375 mg per day (divided in a three-times-a-day schedule) demonstrated superiority of venlafaxine hydrochloride tablets over placebo based on the HAM-D-21 total score. The mean dose in completers was 350 mg per day (study 3).

In a longer-term study, adult outpatients with MDD who had responded during an 8-week open-label study on venlafaxine hydrochloride extended-release capsules (75, 150, or 225 mg, once daily every morning) were randomized to continuation of their same venlafaxine hydrochloride extended-release capsules dose or to placebo, for up to 26 weeks of observation for relapse. Response during the open-label phase was defined as a CGI Severity of Illness item score of ≤3 and a HAM-D-21 total score of ≤10 at the day 56 evaluation. Relapse during the double-blind phase was defined as follows: (1) a reappearance of major depressive disorder as defined by DSM-IV criteria and a CGI Severity of Illness item score of ≥4 (moderately ill), (2) 2 consecutive CGI Severity of Illness item scores of ≥4, or (3) a final CGI Severity of Illness item score of ≥4 for any patient who withdrew from the study for any reason.

Patients receiving continued venlafaxine hydrochloride extended-release capsules treatment experienced statistically significantly lower relapse rates over the subsequent 26 weeks compared with those receiving placebo (study 4).

In a second longer term trial, adult outpatients with MDD, recurrent type, who had responded (HAM-D 21 total score ≤ 12 at the day 56 evaluation) and continued to be improved [defined as the following criteria being met for days 56 through 180: (1) no HAM-D-21 total score ≥ 20; (2) no more than 2 HAM D-21 total scores > 10, and (3) no single CGI Severity of Illness item score ≥ 4 (moderately ill)] during an initial 26 weeks of treatment on venlafaxine hydrochloride tablets [100 to 200 mg per day, on a twice daily schedule] were randomized to continuation of their same venlafaxine hydrochloride tablets dose or to placebo. The follow-up period to observe patients for relapse, defined as a CGI Severity of Illness item score ≥ 4, was for up to 52 weeks. Patients receiving continued venlafaxine hydrochloride tablets treatment experienced statistically significantly lower relapse rates over the subsequent 52 weeks compared with those receiving placebo (study 5).

Table 17 Major Depressive Disorder Studies

SD: standard deviation; LS Mean: least-squares mean; CI: confidence interval.

a Difference (drug minus placebo) in least-squares mean change from baseline

* Doses statistically significantly superior to placebo.

Study Number
Treatment
Group
Primary Efficacy Measure: HAM-D Score
Mean Baseline Score (SD)
LS Mean Change from Baseline
Placebo Subtracted Differencea (95%CI)
Study 1
Venlafaxine Hydrochloride Extended-release Capsules (75 to 225 mg/day)*
24.5
-11.7
-4.45(-6.66,-2.25)
Placebo
23.6
-7.24
-
Study 2
Venlafaxine Hydrochloride Extended-release Capsules (75 to 225 mg/day)*
24.5
-15.11
-6.40(-8.45,-4.34)
Placebo
24.9
-8.71
-
Study 3
Venlafaxine Hydrochloride Tablets (150 to 375 mg/day)*
28.2 (0.5)
-14.9
-10.2 (-14.4,-6)
Placebo
28.6 (0.6)
-4.7
-

14.2 Generalized Anxiety Disorder

The efficacy of venlafaxine hydrochloride extended-release capsules as a treatment for Generalized Anxiety Disorder (GAD) was established in two 8-week, placebo-controlled, fixed-dose studies (75 to 225 mg per day), one 6-month, placebo-controlled, flexible-dose study (75 to 225 mg per day), and one 6-month, placebo-controlled, fixed-dose study (37.5, 75, and 150 mg per day) in adult outpatients meeting DSM-IV criteria for GAD.

In one 8-week study, venlafaxine hydrochloride extended-release capsules demonstrated superiority over placebo for the 75, 150, and 225 mg per day doses as measured by the Hamilton Rating Scale for Anxiety (HAM-A) total score, both the HAM-A anxiety and tension items, and the Clinical Global Impressions (CGI) scale. However, the 75 and 150 mg per day doses were not as consistently effective as the highest dose (study 1). A second 8-week study evaluating doses of 75 and 150 mg per day and placebo showed that both doses were more effective than placebo on some of these same outcomes; however, the 75 mg per day dose was more consistently effective than the 150 mg per day dose (study 2). A dose-response relationship for effectiveness in GAD was not clearly established in the 75 to 225 mg per day dose range studied.

Two 6-month studies, one evaluating venlafaxine hydrochloride extended-release capsules doses of 37.5, 75, and 150 mg per day (study 3) and the other evaluating venlafaxine hydrochloride extended-release capsules doses of 75 to 225 mg per day (study 4), showed that daily doses of 75 mg or higher were more effective than placebo on the HAM-A total, both the HAM-A anxiety and tension items, and the CGI scale during 6 months of treatment. While there was also evidence for superiority over placebo for the 37.5 mg per day dose, this dose was not as consistently effective as the higher doses.

Examination of gender subsets of the population studied did not reveal any differential responsiveness on the basis of gender.

Table 18 Generalized Anxiety Disorder Studies

SD: standard deviation; SE: standard error; LS Mean: least-squares mean; CI: confidence interval.

aDoses statistically significantly superior to placebo.

*Difference (drug minus placebo) in least-squares mean change from baseline

Study Number
Treatment Group
Primary Efficacy Measure: HAM-A Score
Mean Baseline Score (SD)
LS Mean Change from Baseline (SE)
Placebo Subtracted Differencea (95% CI)
Study 1
Ven XR 75 mg
24.7
-11.1 (0.95)
-1.5 (-3.8, 0.8)
Ven XR 150 mg
24.5
-11.7 (0.87)
-2.2 (-4.5, 0.1)
Eff XR 225 mg
23.6
-12.1 (0.81)
-2.6 (-4.9, -0.3)
Placebo
24.1
-9.5 (0.85)
Study 2
Ven XR 75 mg
23.7
-10.6 (0.82)
-2.6 (-4.6, -0.5)
Ven XR 150 mg
23.0
-9.8 (0.86)
-1.7 (-3.8, 0.3)
Placebo
23.7
-8.0 (0.73)
Study 3
Ven XR 37.5 mg
26.6 (0.4)
-13.8
-2.8 (-5.1, -0.6)
Ven XR 75 mg
26.3 (0.4)
-15.5
-4.6 (-6.9, -2.3)
Ven XR150 mg
26.3 (0.4)
-16.4
-5.5 (-7.8, -3.1)
Placebo
26.7 (0.5)
-11.0
Study 4
Ven XR 75 to 225 mg
25.0
-13.4 (0.79)
- 4.7 (-6.6, -2.9)
Placebo
24.9
-8.7 (0.70)

14.3 Social Anxiety Disorder (also known as Social Phobia)

The efficacy of venlafaxine hydrochloride extended-release capsules as a treatment for Social Anxiety Disorder (SAD) was established in four double-blind, parallel-group, 12-week, multicenter, placebo-controlled, flexible-dose studies (studies 1-4) and one double-blind, parallel-group, 6-month, placebo-controlled, fixed/flexible-dose study, which included doses in a range of 75 to 225 mg per day in adult outpatients meeting DSM-IV criteria for SAD (study 5).

In these five studies, venlafaxine hydrochloride extended-release capsule was statistically significantly more effective than placebo on change from baseline to endpoint on the Liebowitz Social Anxiety Scale (LSAS) total score. There was no evidence for any greater effectiveness of the 150 to 225 mg per day group compared to the 75 mg per day group in the 6-month study.

Examination of subsets of the population studied did not reveal any differential responsiveness on the basis of gender. There was insufficient information to determine the effect of age or race on outcome in these studies.

Table 19 Social Anxiety Disorder Studies

SD: standard deviation; SE: standard error; LS Mean: least-squares mean; CI: confidence interval.

a Difference (drug minus placebo) in least-squares mean change from baseline

* Doses statistically significantly superior to placebo.

Study Number
Treatment Group
Primary Efficacy Measure: LSAS Score
Mean Baseline Score
(SD)
LS Mean Change from Baseline
(SE)
Placebo Subtracted Differencea
(95% CI)
Study 1
Ven XR (75 to 225 mg) Placebo
91.1
86.7
-31(2.22)
-19.9 (2.22)
11.2 (-5.3, -17.1)
-
Study 2
Ven XR (75 to 225 MG) Placebo
90.8
87.4
-32.8 (2.69)
-22.1 (2.66)
-10.7 (-3.7,-17.6)
-
Study 3
Ven XR (75 to 225 MG) Placebo
83.2
83.6
-36 (2.35)
-19.1 (2.40)
-16.9(-22.6, -11.2)
-12.7 (-6.5, -19)
Study 4
Ven XR (75 to 225 mg) Placebo
86.2
86.1
-35 (2.64)
-22.2 (2,47)
-14.6 (-21.8, -7.4)
-
Study 5
Ven XR 75 mg
91.8
-38.1 (3.16)
-14.6 (-21.8, -7.4)
Ven XR (150 to 225 mg)
86.2
-37.6 (3.05)
-14.1 (-21.3, -6.9)
Placebo
89.3
-23.5 (3.08)
-

14.4 Panic Disorder

The efficacy of venlafaxine hydrochloride extended-release capsules as a treatment for Panic Disorder (PD) was established in two double-blind, 12-week, multicenter, placebo-controlled studies in adult outpatients meeting DSM-IV criteria for PD, with or without agoraphobia. Patients received fixed doses of 75 or 150 mg per day in one study (study 1) and 75 or 225 mg per day in the other study (study 2).

Efficacy was assessed on the basis of outcomes in three variables: (1) percentage of patients free of full- symptom panic attacks on the Panic and Anticipatory Anxiety Scale (PAAS); (2) mean change from baseline to endpoint on the Panic Disorder Severity Scale (PDSS) total score; and (3) percentage of patients rated as responders (much improved or very much improved) on the Clinical Global Impressions (CGI) Improvement scale. In these two studies, venlafaxine hydrochloride extended-release capsule was statistically significantly more effective than placebo (for each fixed dose) on all three endpoints, but a dose-response relationship was not clearly established.

Examination of subsets of the population studied did not reveal any differential responsiveness on the basis of gender. There was insufficient information to determine the effect of age or race on outcome in these studies.

In a longer term study (study 3), adult outpatients meeting DSM-IV criteria for PD who had responded during a 12-week open phase with venlafaxine hydrochloride extended-release capsules (75 to 225 mg per day) were randomly assigned to continue the same venlafaxine hydrochloride extended-release capsules dose (75, 150, or 225 mg) or switch to placebo for observation for relapse under double-blind conditions. Response during the open phase was defined as ≤ 1 full-symptom panic attack per week during the last 2 weeks of the open phase and a CGI Improvement score of 1 (very much improved) or 2 (much improved). Relapse during the double-blind phase was defined as having 2 or more full-symptom panic attacks per week for 2 consecutive weeks or having discontinued due to loss of effectiveness as determined by the investigators during the study. Randomized patients were in response status for a mean time of 34 days prior to being randomized. In the randomized phase following the 12 week open-label period, patients receiving continued venlafaxine hydrochloride extended-release capsules experienced a statistically significantly longer time to relapse.

Table 20 Panic Disorder Studies

aOdds ratio (drug to placebo) in terms of probability of free of full-symptom panic attacks based on logistic regression model.

95%CI: 95% confidence interval without adjusting for multiple dose arms.

*Doses statistically significantly superior to placebo.

Study Number
Treatment
Group
Primary Efficacy Measure: Whether Free of Full-symptom Panic Attacks
Percent of patients Free of Full symptom panic attack
Adjusted Odds
Ratioa
to placebo
Adjusted Odds Ratioa 95% Confidence Interval
Study 1
Ven XR 75 mg* Ven XR 150 mg* Placebo
54.1% (85/157)
61.4% (97/158)
34.4% (53/154)
2. 268
3.035
-
(1.43, 3.59)
(1.91, 4.82)
-
Study 2
Ven XR 75 mg* Ven XR 225 mg* Placebo
64.1% (100/156)
70% (112/160)
46.5% (73/157)
2.350
2.890
-
(1.46, 3.78)
(1.80, 4.64)
-

14.5 Pediatric Patients

Two placebo-controlled studies in 766 pediatric patients with MDD and two placebo-controlled studies in 793 pediatric patients with GAD have been conducted with venlafaxine hydrochloride extended-release capsules, and the data were not sufficient to support a claim for use in pediatric patients.

See FDA-approved patient labeling (Medication Guide).

Prescribers or other healthcare professionals should inform patients, their families, and their caregivers about the benefits and risks associated with treatment with venlafaxine hydrochloride extended-release capsules and should counsel them in its appropriate use. A patient Medication Guide about "Antidepressant Medicines, Depression and Other Serious Mental Illnesses, and Suicidal Thoughts or Actions" is available for venlafaxine hydrochloride extended-release capsules. The prescriber or healthcare professional should instruct patients, their families, and their caregivers to read the Medication Guide and should assist them in understanding its contents. Patients should be given the opportunity to discuss the contents of the Medication Guide and to obtain answers to any questions they may have. The complete text of the Medication Guide is reprinted at the end of this document. Patients should be advised of the following issues and should be asked to alert their prescriber if these occur while taking venlafaxine hydrochloride extended-release capsules.

Suicidal Thoughts and Behaviors

Advise patients, their families and caregivers to look for the emergence of suicidality, worsening of depression, and other psychiatric symptoms (anxiety, agitation, panic attacks, insomnia, irritability, hostility, aggressiveness, impulsivity, akathisia, psychomotor restlessness, hypomania, mania, other unusual changes in behavior), especially early during treatment and when the dose is adjusted up or down. Such symptoms should be reported to the patient's prescriber or health professional, especially if they are severe, abrupt in onset, or were not part of the patient's presenting symptoms. Symptoms such as these may be associated with an increased risk for suicidal thinking and behavior and indicate a need for very close monitoring [see Boxed Warning and Warnings and Precautions (5.1)].

Concomitant Medication

Advise patients taking venlafaxine hydrochloride extended-release capsules not to use concomitantly other products containing venlafaxine or desvenlafaxine. Healthcare professionals should instruct patients not to take venlafaxine hydrochloride extended-release capsules with an MAOI or within 14 days of stopping an MAOI and to allow 7 days after stopping venlafaxine hydrochloride extended-release capsules before starting an MAOI [see Contraindications (4.2)].

Serotonin Syndrome

Patients should be cautioned about the risk of serotonin syndrome, with the concomitant use of venlafaxine hydrochloride extended-release capsules and triptans, tramadol, amphetamines, tryptophan supplements, with antipsychotics or other dopamine antagonists, or other serotonergic agents [see Warnings and Precautions (5.2) and Drug Interactions (7.3)].

Elevated Blood Pressure

Advise patients that they should have regular monitoring of blood pressure when taking venlafaxine hydrochloride extended-release capsules [see Warnings and Precautions (5.3)].

Abnormal Bleeding

Patients should be cautioned about the concomitant use of venlafaxine hydrochloride extended-release capsules and NSAIDs, aspirin, warfarin, or other drugs that affect coagulation since combined use of psychotropic drugs that interfere with serotonin reuptake and these agents has been associated with an increased risk of bleeding [see Warnings and Precautions (5.4)].

Angle Closure Glaucoma

Patients should be advised that taking venlafaxine hydrochloride extended-release capsules can cause mild pupillary dilation, which in susceptible individuals, can lead to an episode of angle closure glaucoma. Preexisting glaucoma is almost always open-angle glaucoma because angle closure glaucoma, when diagnosed, can be treated definitively with iridectomy. Open-angle glaucoma is not a risk factor for angle closure glaucoma. Patients may wish to be examined to determine whether they are susceptible to angle closure, and have a prophylactic procedure (e.g., iridectomy), if they are susceptible [see Warnings and Precautions (5.5)].

Activation of Mania/Hypomania

Advise patients, their families and caregivers to observe for signs of activation of mania/hypomania [see Warnings and Precautions (5.6)].

Cardiovascular/Cerebrovascular Disease

Caution is advised in administering venlafaxine hydrochloride extended-release capsules to patients with cardiovascular, cerebrovascular, or lipid metabolism disorders [see Adverse Reactions (6.1)].

Serum Cholesterol and Triglyceride Elevation

Advise patients that elevations in total cholesterol, LDL and triglycerides may occur and that measurement of serum lipids may be considered [see Warnings and Precautions (6.3)].

Discontinuation [Symptoms]

Advise patients not to stop taking venlafaxine hydrochloride extended-release capsules without talking first with their healthcare professional. Patients should be aware that discontinuation effects may occur when stopping venlafaxine hydrochloride extended-release capsules [see Warnings and Precautions (5.7) and Adverse Reactions (6.1)].

Interference with Cognitive and Motor Performance

Caution patients about operating hazardous machinery, including automobiles, until they are reasonably certain that venlafaxine hydrochloride extended-release capsules therapy does not adversely affect their ability to engage in such activities.

Alcohol

Advise patients to avoid alcohol while taking venlafaxine hydrochloride extended-release capsules [see Drug Interactions (7.6)].

Allergic Reactions

Advise patients to notify their physician if they develop allergic phenomena such as rash, hives, swelling, or difficulty breathing.

Pregnancy

Advise patients to notify their physician if they become pregnant or intend to become pregnant during therapy [see Use in Specific Populations (8.1)].

Nursing

Advise patients to notify their physician if they are breast-feeding an infant [see Use in Specific Populations (8.3)].

Residual Spheroids

Venlafaxine hydrochloride extended-release capsule contains spheroids, which release the drug slowly into the digestive tract. The insoluble portion of these spheroids is eliminated, and patients may notice spheroids passing in the stool or via colostomy. Patients should be informed that the active medication has already been absorbed by the time the patient sees the spheroids.

Manufactured by:

Cadila Healthcare Ltd.

Ahmedabad, India

Distributed by:

Zydus Pharmaceuticals (USA) Inc.

Pennington, NJ 08534

Rev.: 12/17